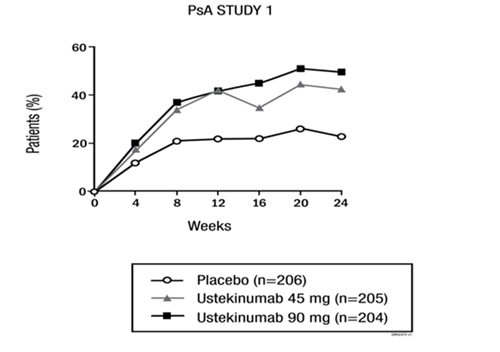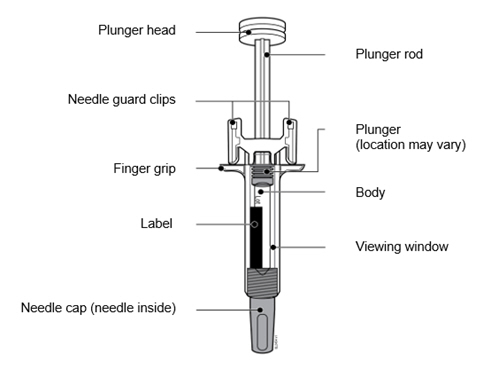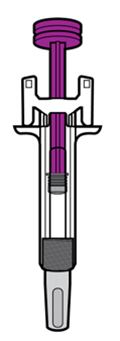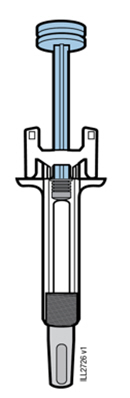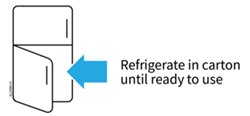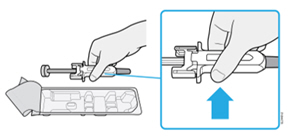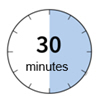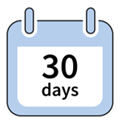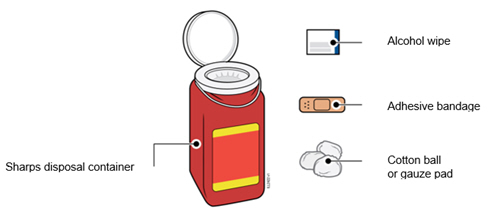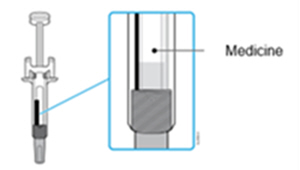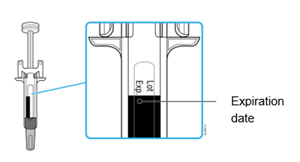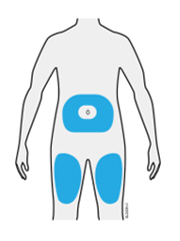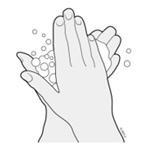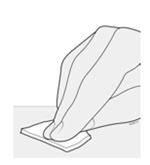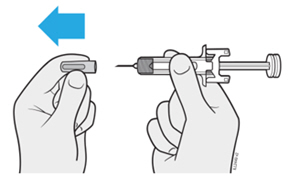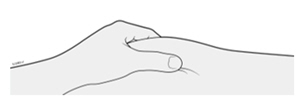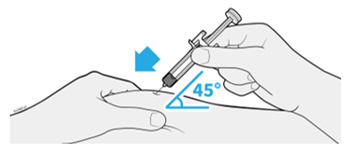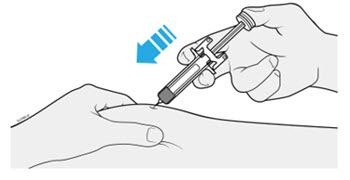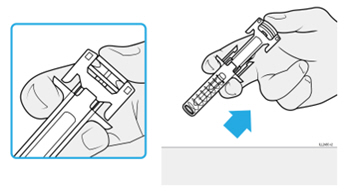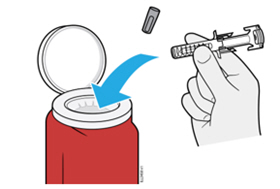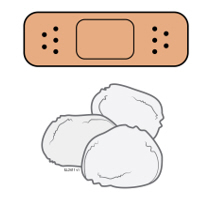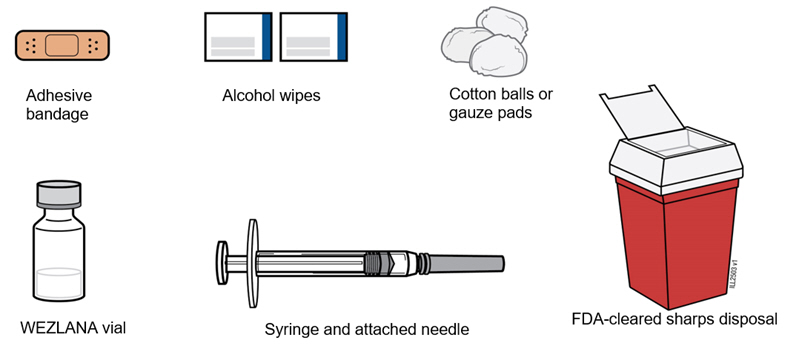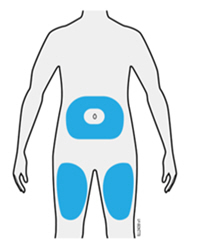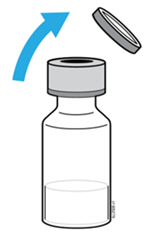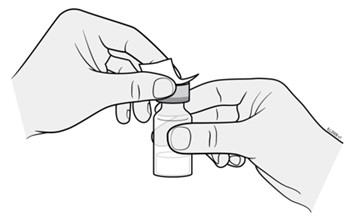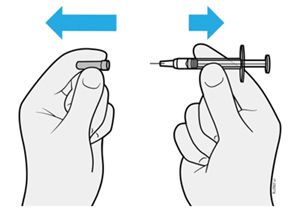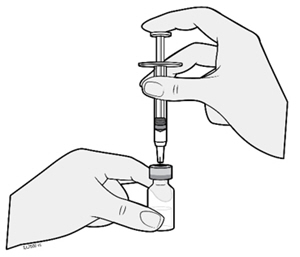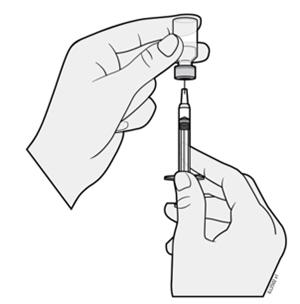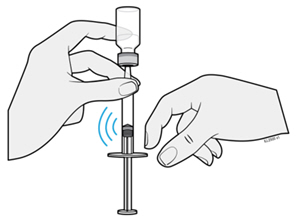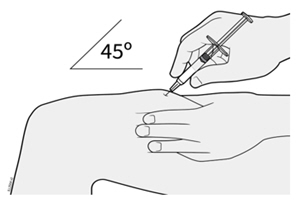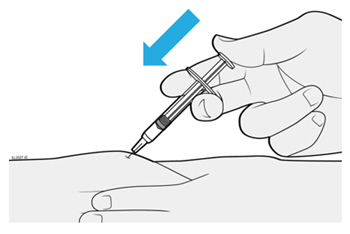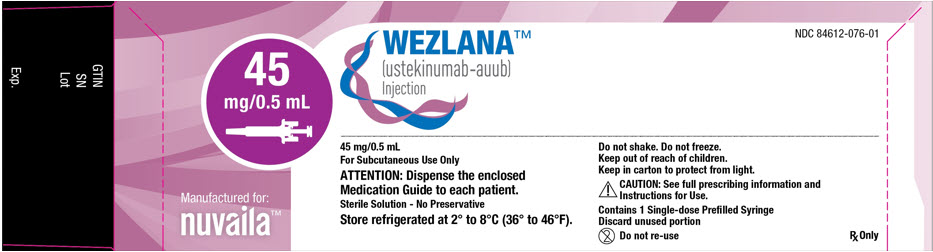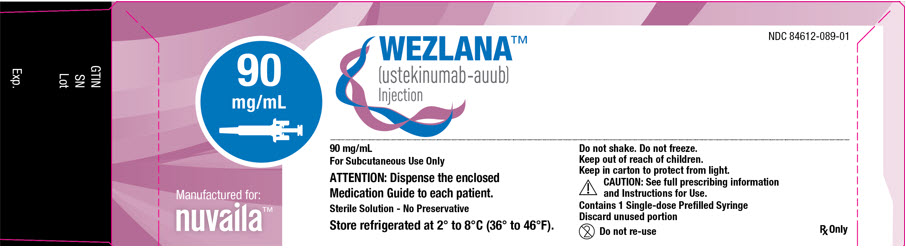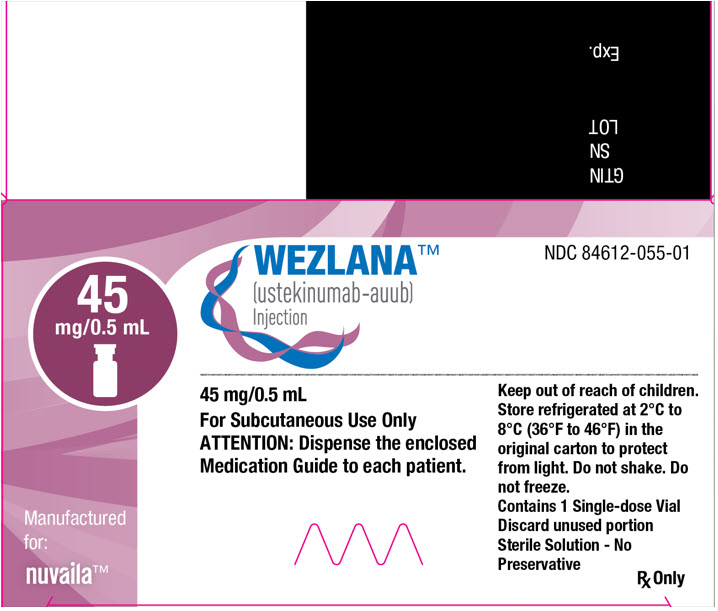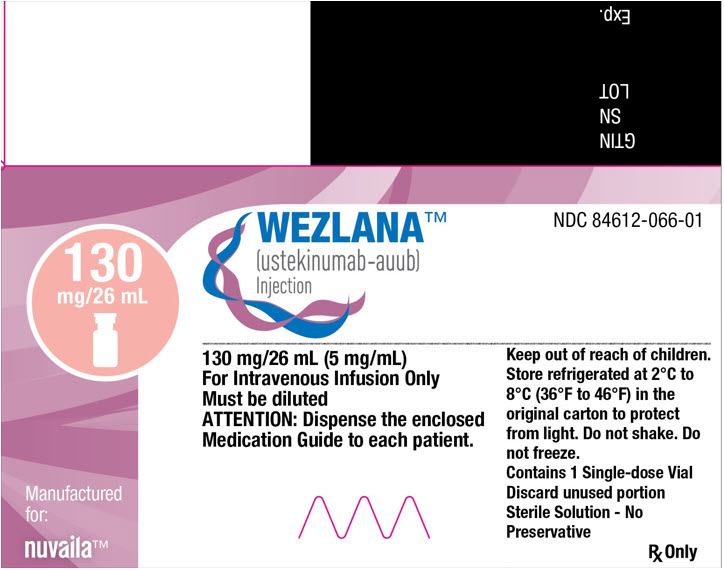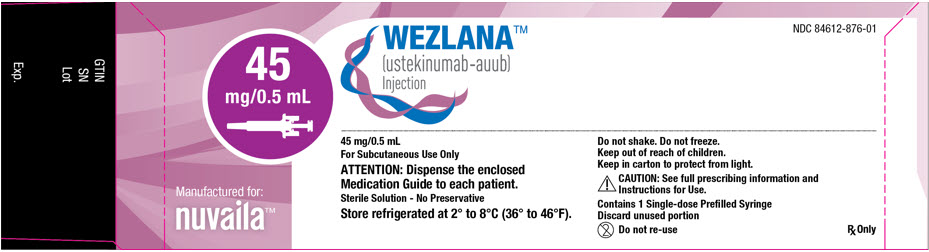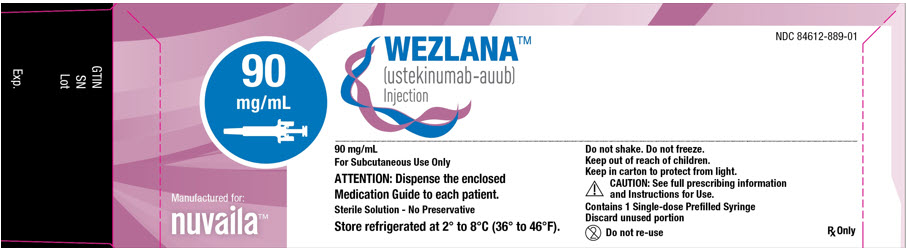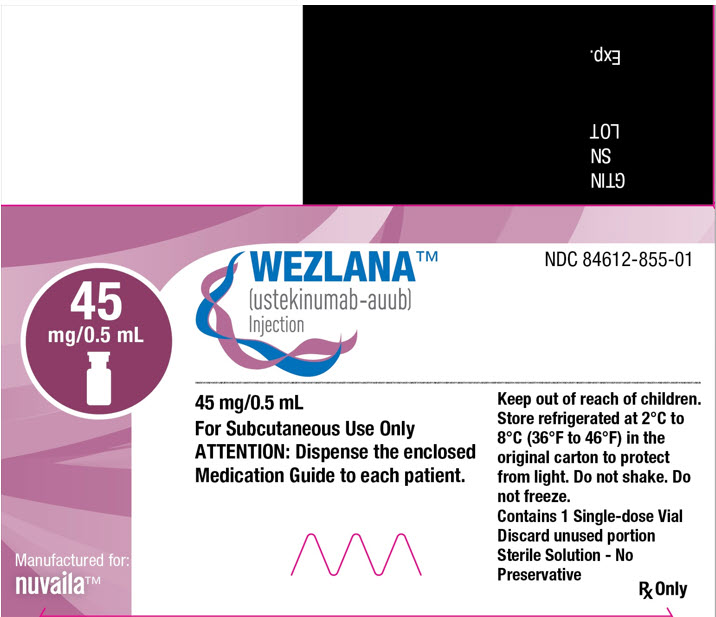 DRUG LABEL: WEZLANA
NDC: 84612-076 | Form: INJECTION, SOLUTION
Manufacturer: Nuvaila Limited
Category: prescription | Type: HUMAN PRESCRIPTION DRUG LABEL
Date: 20260208

ACTIVE INGREDIENTS: USTEKINUMAB 45 mg/0.5 mL
INACTIVE INGREDIENTS: HISTIDINE 0.23 mg/0.5 mL; HISTIDINE HYDROCHLORIDE MONOHYDRATE 0.36 mg/0.5 mL; POLYSORBATE 80 0.02 mg/0.5 mL; SUCROSE 38 mg/0.5 mL

HIGHLIGHTS OF PRESCRIBING INFORMATION

These highlights do not include all the information needed to use WEZLANA™ safely and effectively. See full prescribing information for WEZLANA.
WEZLANA™ (ustekinumab-auub) injection, for subcutaneous or intravenous use
Initial U.S. Approval: 2023
WEZLANA™ (ustekinumab-auub) is biosimilar [Biosimilar means that the biological product is approved based on data demonstrating that it is highly similar to an FDA-approved biological product known as a reference product, and that there are no clinically meaningful differences between the biosimilar product and the reference product. Biosimilarity of WEZLANA has been demonstrated for the condition(s) of use (e.g., indication(s), dosing regimen(s), strength(s), dosage form(s), and route(s) of administration described in its Full Prescribing Information.] to STELARA® (ustekinumab).

1 INDICATIONS AND USAGE

WEZLANA is a human interleukin -12 and -23 antagonist indicated for the treatment of:

Adult patients with:

- moderate to severe plaque psoriasis (PsO) who are candidates for phototherapy or systemic therapy. (1.1)
- active psoriatic arthritis (PsA). (1.2)
- moderately to severely active Crohn's disease (CD). (1.3)
- moderately to severely active ulcerative colitis. (1.4)

Pediatric patients 6 years and older with:

- moderate to severe plaque psoriasis (PsO), who are candidates for phototherapy or systemic therapy. (1.1)
- active psoriatic arthritis (PsA). (1.2)

2 DOSAGE AND ADMINISTRATION

Adult Patients with Plaque Psoriasis Subcutaneous Recommended Dosage (2.1):

Weight Range (kilograms) | Dosage
less than or equal to 100 kg | 45 mg administered subcutaneously initially and 4 weeks later, followed by 45 mg administered subcutaneously every 12 weeks
greater than 100 kg | 90 mg administered subcutaneously initially and 4 weeks later, followed by 90 mg administered subcutaneously every 12 weeks

Pediatric Patients 6 Years of Age and Older with Plaque Psoriasis Subcutaneous Recommended Dosage (2.1):

Weight-based dosing is recommended at the initial dose, 4 weeks later, then every 12 weeks thereafter.

Weight Range (kilograms) | Dose
less than 60 kg | 0.75 mg/kg
60 kg to 100 kg | 45 mg
greater than 100 kg | 90 mg

Psoriatic Arthritis Adult Subcutaneous Recommended Dosage (2.2):

- The recommended dosage is 45 mg administered subcutaneously initially and 4 weeks later, followed by 45 mg administered subcutaneously every 12 weeks.
- For patients with co-existent moderate-to-severe plaque psoriasis weighing greater than 100 kg, the recommended dosage is 90 mg administered subcutaneously initially and 4 weeks later, followed by 90 mg administered subcutaneously every 12 weeks.

Psoriatic Arthritis Pediatric 6 Years of Age and Older Subcutaneous Recommended Dosage (2.2): Weight-based dosing is recommended at the initial dose, 4 weeks later, then every 12 weeks thereafter.

Weight Range (kilograms) | Dose
less than 60 kg | 0.75 mg/kg
60 kg or more | 45 mg
greater than 100 kg with co- existent moderate-to-severe plaque psoriasis | 90 mg

Crohn's Disease and Ulcerative Colitis Initial Adult Intravenous Recommended Dose (2.3):

A single intravenous infusion using weight-based dosing:

Weight Range (kilograms) | Recommended Dose
up to 55 kg | 260 mg (2 vials)
greater than 55 kg to 85 kg | 390 mg (3 vials)
greater than 85 kg | 520 mg (4 vials)

Crohn's Disease and Ulcerative Colitis Maintenance Adult Subcutaneous Recommended Dosage (2.3):

A subcutaneous 90 mg dose 8 weeks after the initial intravenous dose, then every 8 weeks thereafter.

3 DOSAGE FORMS AND STRENGTHS

Subcutaneous Injection (3)

- Injection: 45 mg/0.5 mL or 90 mg/mL solution in a single-dose prefilled syringe
- Injection: 45 mg/0.5 mL solution in a single-dose vial

Intravenous Infusion (3)

- Injection: 130 mg/26 mL (5 mg/mL) solution in a single-dose vial

4 CONTRAINDICATIONS

Clinically significant hypersensitivity to ustekinumab products or to any of the excipients in WEZLANA. (4)

5 WARNINGS AND PRECAUTIONS

- Infections: Serious infections have occurred. Avoid starting WEZLANA during any clinically important active infection. If a serious infection or clinically significant infection develops, discontinue WEZLANA until the infection resolves. (5.1)
- Theoretical Risk for Particular Infections: Serious infections from mycobacteria, salmonella, and Bacillus Calmette-Guerin (BCG) vaccinations have been reported in patients genetically deficient in IL-12/IL-23. Consider diagnostic tests for these infections as dictated by clinical circumstances. (5.2)
- Tuberculosis (TB): Evaluate patients for TB prior to initiating treatment with WEZLANA. Initiate treatment of latent TB before administering WEZLANA. (5.3)
- Malignancies: Ustekinumab products may increase risk of malignancy. The safety of ustekinumab products in patients with a history of or a known malignancy has not been evaluated. (5.4)
- Hypersensitivity Reactions: If an anaphylactic or other clinically significant hypersensitivity reaction occurs, institute appropriate therapy and discontinue WEZLANA. (5.5)
- Posterior Reversible Encephalopathy Syndrome (PRES): If PRES is suspected, treat promptly, and discontinue WEZLANA. (5.6)
- Immunizations: Avoid use of live vaccines in patients during treatment with WEZLANA. (5.7)
- Noninfectious Pneumonia: Cases of interstitial pneumonia, eosinophilic pneumonia and cryptogenic organizing pneumonia have been reported during post-approval use of ustekinumab products. If diagnosis is confirmed, discontinue WEZLANA and institute appropriate treatment. (5.8)

6 ADVERSE REACTIONS

Most common adverse reactions are:

- Psoriasis and Psoriatic Arthritis (≥ 3%): nasopharyngitis, upper respiratory tract infection, headache, and fatigue. (6.1)
- Crohn's Disease, induction (≥ 3%): vomiting. (6.1)
- Crohn's Disease, maintenance (≥ 3%): nasopharyngitis, injection site erythema, vulvovaginal candidiasis/mycotic infection, bronchitis, pruritus, urinary tract infection, and sinusitis. (6.1)
- Ulcerative colitis, induction (≥ 3%): nasopharyngitis. (6.1)
- Ulcerative colitis, maintenance (≥ 3%): nasopharyngitis, headache, abdominal pain, influenza, fever, diarrhea, sinusitis, fatigue, and nausea. (6.1)

To report SUSPECTED ADVERSE REACTIONS, contact Amgen Medical Information at 1-800-77-AMGEN (1-800-772-6436) or FDA at 1-800-FDA-1088 or www.fda.gov/medwatch.

FULL PRESCRIBING INFORMATION

1 INDICATIONS AND USAGE

1.1 Plaque Psoriasis (PsO)

WEZLANA is indicated for the treatment of adults and pediatric patients 6 years of age and older with moderate to severe plaque psoriasis who are candidates for phototherapy or systemic therapy.

1.2 Psoriatic Arthritis (PsA)

WEZLANA is indicated for the treatment of adults and pediatric patients 6 years of age and older with active psoriatic arthritis.

1.3 Crohn's Disease (CD)

WEZLANA is indicated for the treatment of adult patients with moderately to severely active Crohn's disease.

1.4 Ulcerative Colitis

WEZLANA is indicated for the treatment of adult patients with moderately to severely active ulcerative colitis.

2 DOSAGE AND ADMINISTRATION

2.1 Recommended Dosage in Plaque Psoriasis

Subcutaneous Adult Dosage Regimen

- For patients weighing 100 kg or less, the recommended dosage is 45 mg initially and 4 weeks later, followed by 45 mg every 12 weeks.
- For patients weighing more than 100 kg, the recommended dosage is 90 mg initially and 4 weeks later, followed by 90 mg every 12 weeks.

In subjects weighing more than 100 kg, 45 mg was also shown to be efficacious. However, 90 mg resulted in greater efficacy in these subjects [see Clinical Studies (14)].

Subcutaneous Pediatric Dosage Regimen

Administer WEZLANA subcutaneously at Weeks 0 and 4, then every 12 weeks thereafter.

The recommended dose of WEZLANA for pediatric patients 6 years of age and older with plaque psoriasis based on body weight is shown below (Table 1).

Table 1. Recommended Dose of WEZLANA for Subcutaneous Injection in Pediatric Patients 6 Years of Age and Older with Plaque Psoriasis
Body Weight of Patient at the Time of Dosing | Recommended Dose
less than 60 kg | 0.75 mg/kg
60 kg to 100 kg | 45 mg
more than 100 kg | 90 mg

For pediatric patients weighing less than 60 kg, the administration volume for the recommended dose (0.75 mg/kg) is shown in Table 2; withdraw the appropriate volume from the vial.

Table 2. Injection Volumes of WEZLANA 45 mg/0.5 mL Vials for Pediatric Patients 6 Years of Age and Older with Plaque Psoriasis and Pediatric Patients 6 Years of Age and Older with Psoriatic Arthritis [Refer to 2.2 Psoriatic Arthritis; Subcutaneous Pediatric Dosage Regimen.] Weighing Less Than 60 kg
Body Weight (kg) at the time of dosing | Dose (mg) | Volume of injection (mL)
15 | 11.3 | 0.12
16 | 12 | 0.13
17 | 12.8 | 0.14
18 | 13.5 | 0.15
19 | 14.3 | 0.16
20 | 15 | 0.17
21 | 15.8 | 0.17
22 | 16.5 | 0.18
23 | 17.3 | 0.19
24 | 18 | 0.20
25 | 18.8 | 0.21
26 | 19.5 | 0.22
27 | 20.3 | 0.22
28 | 21 | 0.23
29 | 21.8 | 0.24
30 | 22.5 | 0.25
31 | 23.3 | 0.26
32 | 24 | 0.27
33 | 24.8 | 0.27
34 | 25.5 | 0.28
35 | 26.3 | 0.29
36 | 27 | 0.30
37 | 27.8 | 0.31
38 | 28.5 | 0.32
39 | 29.3 | 0.32
40 | 30 | 0.33
41 | 30.8 | 0.34
42 | 31.5 | 0.35
43 | 32.3 | 0.36
44 | 33 | 0.37
45 | 33.8 | 0.37
46 | 34.5 | 0.38
47 | 35.3 | 0.39
48 | 36 | 0.40
49 | 36.8 | 0.41
50 | 37.5 | 0.42
51 | 38.3 | 0.42
52 | 39 | 0.43
53 | 39.8 | 0.44
54 | 40.5 | 0.45
55 | 41.3 | 0.46
56 | 42 | 0.46
57 | 42.8 | 0.47
58 | 43.5 | 0.48
59 | 44.3 | 0.49

2.2 Recommended Dosage in Psoriatic Arthritis

Subcutaneous Adult Dosage Regimen

- The recommended dosage is 45 mg initially and 4 weeks later, followed by 45 mg every 12 weeks.
- For patients with co-existent moderate-to-severe plaque psoriasis weighing more than 100 kg, the recommended dosage is 90 mg initially and 4 weeks later, followed by 90 mg every 12 weeks.

Subcutaneous Pediatric Dosage Regimen

Administer WEZLANA subcutaneously at Weeks 0 and 4, then every 12 weeks thereafter.

The recommended dose of WEZLANA for pediatric patients 6 years of age and older with psoriatic arthritis, based on body weight, is shown below (Table 3).

Table 3. Recommended Dose of WEZLANA for Subcutaneous Injection in Pediatric Patients 6 Years of Age and Older with Psoriatic Arthritis
Body Weight of Patient at the Time of Dosing | Recommended Dose
less than 60 kg [For pediatric patients weighing less than 60 kg, the administration volume for the recommended dose (0.75 mg/kg) is shown in Table 2; withdraw the appropriate volume from the vial.] | 0.75 mg/kg
60 kg or more | 45 mg
greater than 100 kg with co-existent moderate-to-severe plaque psoriasis | 90 mg

2.3 Recommended Dosage in Crohn's Disease and Ulcerative Colitis

Intravenous Induction Adult Dosage Regimen

A single intravenous infusion dose of WEZLANA using the weight-based dosage regimen specified in Table 4 [see Instructions for dilution of WEZLANA 130 mg vial for intravenous infusion (2.5)].

Table 4. Initial Intravenous Dosage of WEZLANA
Body Weight of Patient at the time of dosing | Dose | Number of 130 mg/26 mL (5 mg/mL) WEZLANA vials
55 kg or less | 260 mg | 2
more than 55 kg to 85 kg | 390 mg | 3
more than 85 kg | 520 mg | 4

Subcutaneous Maintenance Adult Dosage Regimen

The recommended maintenance dosage is a subcutaneous 90 mg dose administered 8 weeks after the initial intravenous dose, then every 8 weeks thereafter.

2.4 General Considerations for Administration

- WEZLANA is intended for use under the guidance and supervision of a healthcare provider. WEZLANA should only be administered to patients who will be closely monitored and have regular follow-up visits with a healthcare provider. The appropriate dose should be determined by a healthcare provider using the patient's current weight at the time of dosing. In pediatric patients, it is recommended that WEZLANA be administered by a healthcare provider. If a healthcare provider determines that it is appropriate, a patient may self-inject, or a caregiver may inject WEZLANA after proper training in subcutaneous injection technique. Instruct patients to follow the directions provided in the Instructions for Use [see Instructions for Use].
- The needle cap on the prefilled syringe does not contain dry natural rubber (a derivative of latex).
- It is recommended that each injection be administered at a different anatomic location (such as upper arms, gluteal regions, thighs, or any quadrant of abdomen) than the previous injection, and not into areas where the skin is tender, bruised, erythematous, or indurated. When using the vial, a 1 mL syringe with a 27 gauge, ½ inch needle is recommended.
- Parenteral drug products should be inspected visually for particulate matter and discoloration prior to administration, whenever solution and container permit. WEZLANA is a clear to opalescent and colorless to light yellow solution. Do not use WEZLANA if it is discolored or cloudy, or if other particulate matter is present. WEZLANA does not contain preservatives; therefore, discard any unused product remaining in the vial and/or syringe.

2.5 Preparation and Administration of WEZLANA 130 mg/26 mL (5 mg/mL) Vial for Intravenous Infusion (Crohn's Disease and Ulcerative Colitis)

WEZLANA solution for intravenous infusion must be diluted, prepared and infused by a healthcare professional using aseptic technique.

1. Calculate the dose and the number of WEZLANA vials needed based on patient weight (Table 4). Each 26 mL vial of WEZLANA contains 130 mg of ustekinumab-auub.
2. Withdraw, and then discard a volume of the 0.9% Sodium Chloride Injection, USP from the 250 mL infusion bag equal to the volume of WEZLANA to be added (discard 26 mL sodium chloride for each vial of WEZLANA needed, for 2 vials- discard 52 mL, for 3 vials- discard 78 mL, 4 vials- discard 104 mL). Alternatively, a 250 mL infusion bag containing 0.45% Sodium Chloride Injection, USP may be used.
3. Withdraw 26 mL of WEZLANA from each vial needed and add it to the 250 mL infusion bag. The final volume in the infusion bag should be 250 mL. Gently mix.
4. Visually inspect the diluted solution before infusion. Do not use if visibly opaque particles, discoloration or foreign particles are observed.
5. Infuse the diluted solution over a period of at least one hour. Once diluted, the infusion should be completely administered within eight hours of the dilution in the infusion bag.
6. Use only an infusion set with an in-line, sterile, non-pyrogenic, low protein-binding filter (pore size 0.2 micrometer).
7. Do not infuse WEZLANA concomitantly in the same intravenous line with other agents.
8. WEZLANA does not contain preservatives. Each vial is for a one-time use in only one patient. Discard any remaining solution. Dispose any unused medicinal product in accordance with local requirements.

Storage

If necessary, the diluted infusion solution may be kept at room temperature up to 25°C (77°F) for up to 7 hours. Storage time at room temperature begins once the diluted solution has been prepared. The infusion should be completed within 8 hours after the dilution in the infusion bag (cumulative time after preparation including the storage and the infusion period). Do not freeze. Discard any unused portion of the infusion solution.

3 DOSAGE FORMS AND STRENGTHS

WEZLANA (ustekinumab-auub) is a clear to opalescent and colorless to light yellow solution.

Subcutaneous Injection

- Injection: 45 mg/0.5 mL or 90 mg/mL solution in a single-dose prefilled syringe
- Injection: 45 mg/0.5 mL solution in a single-dose vial

Intravenous Infusion

- Injection: 130 mg/26 mL (5 mg/mL) solution in a single-dose vial

4 CONTRAINDICATIONS

WEZLANA is contraindicated in patients with clinically significant hypersensitivity to ustekinumab products or to any of the excipients in WEZLANA [see Warnings and Precautions (5.5)].

5 WARNINGS AND PRECAUTIONS

5.1 Infections

Ustekinumab products may increase the risk of infections and reactivation of latent infections. Serious bacterial, mycobacterial, fungal, and viral infections were observed in patients receiving ustekinumab products [see Adverse Reactions (6.1, 6.3)].

Serious infections requiring hospitalization, or otherwise clinically significant infections, reported in clinical trials included the following:

- Plaque Psoriasis: diverticulitis, cellulitis, pneumonia, appendicitis, cholecystitis, sepsis, osteomyelitis, viral infections, gastroenteritis and urinary tract infections.
- Psoriatic arthritis: cholecystitis.
- Crohn's disease: anal abscess, gastroenteritis, ophthalmic herpes zoster, pneumonia, and listeria meningitis.
- Ulcerative colitis: gastroenteritis, ophthalmic herpes zoster, pneumonia, and listeriosis.

Avoid initiating treatment with WEZLANA in patients with any clinically important active infection until the infection resolves or is adequately treated. Consider the risks and benefits of treatment prior to initiating use of WEZLANA in patients with a chronic infection or a history of recurrent infection.

Instruct patients to seek medical advice if signs or symptoms suggestive of an infection occur while on treatment with WEZLANA and discontinue WEZLANA for serious or clinically significant infections until the infection resolves or is adequately treated.

5.2 Theoretical Risk for Vulnerability to Particular Infections

Individuals genetically deficient in IL-12/IL-23 are particularly vulnerable to disseminated infections from mycobacteria (including nontuberculous, environmental mycobacteria), salmonella (including nontyphi strains), and Bacillus Calmette-Guerin (BCG) vaccinations. Serious infections and fatal outcomes have been reported in such patients.

It is not known whether patients with pharmacologic blockade of IL-12/IL-23 from treatment with ustekinumab products may be susceptible to these types of infections. Consider appropriate diagnostic testing, (e.g., tissue culture, stool culture, as dictated by clinical circumstances).

5.3 Pre-treatment Evaluation for Tuberculosis

Evaluate patients for tuberculosis infection prior to initiating treatment with WEZLANA.

Avoid administering WEZLANA to patients with active tuberculosis infection. Initiate treatment of latent tuberculosis prior to administering WEZLANA. Consider anti-tuberculosis therapy prior to initiation of WEZLANA in patients with a past history of latent or active tuberculosis in whom an adequate course of treatment cannot be confirmed. Closely monitor patients receiving WEZLANA for signs and symptoms of active tuberculosis during and after treatment.

5.4 Malignancies

Ustekinumab products are immunosuppressants and may increase the risk of malignancy. Malignancies were reported among subjects who received ustekinumab in clinical trials [see Adverse Reactions (6.1)]. In rodent models, inhibition of IL-12/IL-23p40 increased the risk of malignancy [see Nonclinical Toxicology (13)].

The safety of ustekinumab products has not been evaluated in patients who have a history of malignancy or who have a known malignancy.

There have been post-marketing reports of the rapid appearance of multiple cutaneous squamous cell carcinomas in patients receiving ustekinumab products who had pre-existing risk factors for developing non-melanoma skin cancer. Monitor all patients receiving WEZLANA for the appearance of non-melanoma skin cancer. Closely follow patients greater than 60 years of age, those with a medical history of prolonged immunosuppressant therapy and those with a history of PUVA treatment [see Adverse Reactions (6.1)].

5.5 Hypersensitivity Reactions

Hypersensitivity reactions, including anaphylaxis and angioedema, have been reported with ustekinumab products [see Adverse Reactions (6.1, 6.3)]. If an anaphylactic or other clinically significant hypersensitivity reaction occurs, institute appropriate therapy and discontinue WEZLANA.

5.6 Posterior Reversible Encephalopathy Syndrome (PRES)

Two cases of posterior reversible encephalopathy syndrome (PRES), also known as Reversible Posterior Leukoencephalopathy Syndrome (RPLS), were reported in clinical trials. Cases have also been reported in postmarketing experience in patients with psoriasis, psoriatic arthritis, and Crohn's disease. Clinical presentation included headaches, seizures, confusion, visual disturbances, and imaging changes consistent with PRES a few days to several months after ustekinumab product initiation. A few cases reported latency of a year or longer. Patients recovered with supportive care following withdrawal of ustekinumab products.

Monitor all patients treated with WEZLANA for signs and symptoms of PRES. If PRES is suspected, promptly administer appropriate treatment, and discontinue WEZLANA.

5.7 Immunizations

Prior to initiating therapy with WEZLANA, patients should receive all age-appropriate immunizations as recommended by current immunization guidelines. Patients being treated with WEZLANA should avoid receiving live vaccines. Avoid administering BCG vaccines during treatment with WEZLANA or for one year prior to initiating treatment or one year following discontinuation of treatment. Caution is advised when administering live vaccines to household contacts of patients receiving WEZLANA because of the potential risk for shedding from the household contact and transmission to patient.

Non-live vaccinations received during a course of WEZLANA may not elicit an immune response sufficient to prevent disease.

5.8 Noninfectious Pneumonia

Cases of interstitial pneumonia, eosinophilic pneumonia, and cryptogenic organizing pneumonia have been reported during post-approval use of ustekinumab products. Clinical presentations included cough, dyspnea, and interstitial infiltrates following one to three doses. Serious outcomes have included respiratory failure and prolonged hospitalization. Patients improved with discontinuation of therapy and in certain cases administration of corticosteroids. If diagnosis is confirmed, discontinue WEZLANA and institute appropriate treatment [see Postmarketing Experience (6.3)].

6 ADVERSE REACTIONS

The following serious adverse reactions are discussed elsewhere in the label:

- Infections [see Warnings and Precautions (5.1)]
- Malignancies [see Warnings and Precautions (5.4)]
- Hypersensitivity Reactions [see Warnings and Precautions (5.5)]
- Posterior Reversible Encephalopathy Syndrome (PRES) [see Warnings and Precautions (5.6)]
- Noninfectious Pneumonia [see Warnings and Precautions (5.8)]

6.1 Clinical Trials Experience

Because clinical trials are conducted under widely varying conditions, adverse reaction rates observed in the clinical trials of a drug cannot be directly compared to rates in the clinical trials of another drug and may not reflect the rates observed in practice.

Adult Subjects with Plaque Psoriasis

The safety data reflect exposure to ustekinumab in 3117 adult subjects with plaque psoriasis, including 2414 exposed for at least 6 months, 1855 exposed for at least one year, 1653 exposed for at least two years, 1569 exposed for at least three years, 1482 exposed for at least four years and 838 exposed for at least five years.

Table 5 summarizes the adverse reactions that occurred at a rate of at least 1% with higher rates in the ustekinumab groups during the placebo-controlled period of Ps STUDY 1 and Ps STUDY 2 [see Clinical Studies (14)].

Table 5. Adverse Reactions, Reported by ≥ 1% of Subjects with Plaque Psoriasis and at Higher Rates in the Ustekinumab groups through Week 12 in Ps STUDY 1 and Ps STUDY 2
 |  | Ustekinumab
Subjects treated | Placebo 665 | 45 mg 664 | 90 mg 666
Nasopharyngitis | 51 (8%) | 56 (8%) | 49 (7%)
Upper respiratory tract infection | 30 (5%) | 36 (5%) | 28 (4%)
Headache | 23 (3%) | 33 (5%) | 32 (5%)
Fatigue | 14 (2%) | 18 (3%) | 17 (3%)
Back pain | 8 (1%) | 9 (1%) | 14 (2%)
Dizziness | 8 (1%) | 8 (1%) | 14 (2%)
Pharyngolaryngeal pain | 7 (1%) | 9 (1%) | 12 (2%)
Pruritus | 9 (1%) | 10 (2%) | 9 (1%)
Injection site erythema | 3 (< 1%) | 6 (1%) | 13 (2%)
Myalgia | 4 (1%) | 7 (1%) | 8 (1%)
Depression | 3 (< 1%) | 8 (1%) | 4 (1%)

Adverse reactions that occurred at rates less than 1% in the controlled period of Ps STUDIES 1 and 2 through week 12 included: cellulitis, herpes zoster, diverticulitis and certain injection site reactions (pain, swelling, pruritus, induration, hemorrhage, bruising, and irritation).

One case of PRES occurred during clinical trials in adult subjects with plaque psoriasis [see Warnings and Precautions (5.6)].

Infections

In the placebo-controlled period of clinical trials of subjects with plaque psoriasis (average follow-up of 12.6 weeks for subjects receiving placebo and 13.4 weeks for ustekinumab-treated subjects), 27% of ustekinumab-treated subjects reported infections (1.39 per patient-years of follow-up) compared with 24% of subjects receiving placebo (1.21 per patient-years of follow-up). Serious infections occurred in 0.3% of ustekinumab-treated subjects (0.01 per patient-years of follow-up) and in 0.4% of subjects receiving placebo (0.02 per patient-year of follow-up) [see Warnings and Precautions (5.1)].

In the controlled and non-controlled portions of clinical trials in subjects with plaque psoriasis (median follow-up of 3.2 years), representing 8998 patient-years of exposure, 72.3% of ustekinumab-treated subjects reported infections (0.87 per patient-years of follow-up). Serious infections were reported in 2.8% of subjects (0.01 per patient-years of follow-up).

Malignancies

In the controlled and non-controlled portions of clinical trials in subjects with plaque psoriasis (median follow-up of 3.2 years, representing 8998 patient-years of exposure), 1.7% of ustekinumab-treated subjects reported malignancies excluding non-melanoma skin cancers (0.60 per hundred patient-years of follow-up).

Non-melanoma skin cancer was reported in 1.5% of ustekinumab-treated subjects (0.52 per hundred patient-years of follow-up) [see Warnings and Precautions (5.4)]. The most frequently observed malignancies other than non-melanoma skin cancer during the clinical trials were: prostate, melanoma, colorectal and breast. Malignancies other than non-melanoma skin cancer in ustekinumab-treated subjects during the controlled and uncontrolled portions of trials were similar in type and number to what would be expected in the general U.S. population according to the SEER database (adjusted for age, gender and race).^1

Pediatric Subjects with Plaque Psoriasis

The safety of ustekinumab was assessed in two trials of pediatric subjects with moderate to severe plaque psoriasis. Ps STUDY 3 evaluated safety for up to 60 weeks in 110 pediatric subjects 12 to 17 years old. Ps STUDY 4 evaluated safety for up to 56 weeks in 44 pediatric subjects 6 to 11years old. The safety profile in pediatric subjects was similar to the safety profile from trials in adults with plaque psoriasis.

Psoriatic Arthritis

The safety of ustekinumab was assessed in 927 subjects in two randomized, double-blind, placebo-controlled trials in adults with active psoriatic arthritis (PsA). The overall safety profile of ustekinumab in subjects with PsA was consistent with the safety profile seen in clinical trials in adult subjects with plaque psoriasis. A higher incidence of arthralgia, nausea, and dental infections was observed in ustekinumab-treated subjects when compared with placebo-treated subjects (3% vs. 1% for arthralgia and 3% vs. 1% for nausea; 1% vs. 0.6% for dental infections) in the placebo-controlled portions of the PsA clinical trials.

Crohn's Disease

The safety of ustekinumab was assessed in 1407 subjects with moderately to severely active Crohn's disease (Crohn's Disease Activity Index [CDAI] greater than or equal to 220 and less than or equal to 450) in three randomized, double-blind, placebo-controlled, parallel-group, multicenter trials. These 1407 subjects included 40 subjects who received a prior investigational intravenous ustekinumab formulation but were not included in the efficacy analyses. In trials CD-1 and CD-2 there were 470 subjects who received ustekinumab 6 mg/kg as a weight-based single intravenous induction dose and 466 who received placebo [see Dosage and Administration (2.3)]. Subjects who were responders in either trial CD-1 or CD-2 were randomized to receive a subcutaneous maintenance regimen of either 90 mg ustekinumab every 8 weeks, or placebo for 44 weeks in trial CD-3. Subjects in these 3 trials may have received other concomitant therapies including aminosalicylates, immunomodulatory agents [azathioprine (AZA), 6-mercaptopurine (6-MP), methotrexate (MTX)], oral corticosteroids (prednisone or budesonide), and/or antibiotics for their Crohn's disease [see Clinical Studies (14.4)].

The overall safety profile of ustekinumab was consistent with the safety profile seen in the clinical trials in adult subjects with plaque psoriasis and psoriatic arthritis. Common adverse reactions in trials CD-1 and CD-2 and in trial CD-3 are listed in Tables 6 and 7, respectively.

Table 6. Common Adverse Reactions Through Week 8 in Trials CD-1 and CD-2 occurring in ≥ 3% of Ustekinumab-Treated Subjects and Higher Than Subjects Receiving Placebo
 | Placebo N = 466 | Ustekinumab 6 mg/kg single intravenous induction dose N = 470
Vomiting | 3% | 4%

Other less common adverse reactions reported in subjects in trials CD-1 and CD-2 included asthenia (1% vs 0.4%), acne (1% vs 0.4%), and pruritus (2% vs 0.4%).

Table 7. Common Adverse Reactions Through Week 44 in Trial CD-3 occurring in ≥ 3% of Ustekinumab-Treated Subjects and Higher Than Subjects Receiving Placebo
 | Placebo N = 133 | Ustekinumab 90 mg subcutaneous maintenance dose every 8 weeks N = 131
Nasopharyngitis | 8% | 11%
Injection site erythema | 0 | 5%
Vulvovaginal candidiasis/mycotic infection | 1% | 5%
Bronchitis | 3% | 5%
Pruritus | 2% | 4%
Urinary tract infection | 2% | 4%
Sinusitis | 2% | 3%

Infections

In subjects with Crohn's disease, serious or other clinically significant infections included anal abscess, gastroenteritis, and pneumonia. In addition, listeria meningitis and ophthalmic herpes zoster were reported in one subject each [see Warnings and Precautions (5.1)].

Malignancies

With up to one year of treatment in the Crohn's disease clinical trials, 0.2% of ustekinumab-treated subjects (0.36 events per hundred patient-years) and 0.2% of placebo-treated subjects (0.58 events per hundred patient-years) developed non-melanoma skin cancer. Malignancies other than non-melanoma skin cancers occurred in 0.2% of ustekinumab-treated subjects (0.27 events per hundred patient-years) and in none of the placebo-treated subjects.

Hypersensitivity Reactions Including Anaphylaxis

In CD trials, two subjects reported hypersensitivity reactions following ustekinumab administration. One subject experienced signs and symptoms consistent with anaphylaxis (tightness of the throat, shortness of breath, and flushing) after a single subcutaneous administration (0.1% of subjects receiving subcutaneous ustekinumab). In addition, one subject experienced signs and symptoms consistent with or related to a hypersensitivity reaction (chest discomfort, flushing, urticaria, and increased body temperature) after the initial intravenous ustekinumab dose (0.08% of subjects receiving intravenous ustekinumab). These subjects were treated with oral antihistamines or corticosteroids and in both cases symptoms resolved within an hour.

Ulcerative Colitis

The safety of ustekinumab was evaluated in two randomized, double-blind, placebo-controlled clinical trials (UC-1 [IV induction] and UC-2 [SC maintenance]) in 960 adult subjects with moderately to severely active ulcerative colitis [see Clinical Studies (14.5)]. The overall safety profile of ustekinumab in subjects with ulcerative colitis was consistent with the safety profile seen across all approved indications. Adverse reactions reported in at least 3% of ustekinumab-treated subjects and at a higher rate than placebo were:

- Induction (UC-1): nasopharyngitis (7% vs 4%).
- Maintenance (UC-2): nasopharyngitis (24% vs 20%), headache (10% vs 4%), abdominal pain (7% vs 3%), influenza (6% vs 5%), fever (5% vs 4%), diarrhea (4% vs 1%), sinusitis (4% vs 1%), fatigue (4% vs 2%), and nausea (3% vs 2%).

Infections

In subjects with ulcerative colitis, serious or other clinically significant infections included gastroenteritis and pneumonia. In addition, listeriosis and ophthalmic herpes zoster were reported in one subject each [see Warnings and Precautions (5.1)].

Malignancies

With up to one year of treatment in the ulcerative colitis clinical trials, 0.4% of ustekinumab-treated subjects (0.48 events per hundred patient-years) and 0.0% of subjects receiving placebo (0.00 events per hundred patient-years) developed non-melanoma skin cancer. Malignancies other than non-melanoma skin cancers occurred in 0.5% of ustekinumab-treated subjects (0.64 events per hundred patient-years) and 0.2% of subjects receiving placebo (0.40 events per hundred patient-years).

6.2 Immunogenicity

The observed incidence of anti-drug antibodies is highly dependent on the sensitivity and specificity of the assay. Differences in assay methods preclude meaningful comparisons of the incidence of anti-drug antibodies in the studies described below with the incidence of anti-drug antibodies in other studies, including those of ustekinumab or of other ustekinumab products. Approximately 6 to 12.4% of subjects treated with ustekinumab in clinical trials in subjects with plaque psoriasis and psoriatic arthritis developed antibodies to ustekinumab, which were generally low-titer. In clinical trials in subjects with plaque psoriasis, antibodies to ustekinumab were associated with reduced or undetectable serum ustekinumab concentrations and reduced efficacy. In trials in subjects with plaque psoriasis, the majority of subjects who were positive for antibodies to ustekinumab had neutralizing antibodies.

In clinical trials in subjects with Crohn's disease and ulcerative colitis, 2.9% and 4.6% of subjects, respectively, developed antibodies to ustekinumab when treated with ustekinumab for approximately one year. No apparent association between the development of antibodies to ustekinumab and the development of injection site reactions was seen.

6.3 Postmarketing Experience

The following adverse reactions have been reported during post-approval use of ustekinumab products. Because these reactions are reported voluntarily from a population of uncertain size, it is not always possible to reliably estimate their frequency or establish a causal relationship to ustekinumab product exposure.

Immune system disorders: Serious hypersensitivity reactions (including anaphylaxis and angioedema), other hypersensitivity reactions (including rash and urticaria).

Infections and infestations: Lower respiratory tract infection (including opportunistic fungal infections and tuberculosis).

Neurological disorders: Posterior Reversible Encephalopathy Syndrome (PRES).

Respiratory, thoracic, and mediastinal disorders: Interstitial pneumonia, eosinophilic pneumonia, and cryptogenic organizing pneumonia.

Skin reactions: Pustular psoriasis, erythrodermic psoriasis, hypersensitivity vasculitis.

7 DRUG INTERACTIONS

7.1 Concomitant Therapies

In trials in subjects with plaque psoriasis the safety of ustekinumab products in combination with immunosuppressive agents or phototherapy has not been evaluated. In trials in subjects with psoriatic arthritis, concomitant MTX use did not appear to influence the safety or efficacy of ustekinumab. In trials in subjects with Crohn's disease (CD-1 and CD-2) and ulcerative colitis (UC-1), immunomodulators (6-MP, AZA, MTX) were used concomitantly in approximately 30% of subjects and corticosteroids were used concomitantly in approximately 40% and 50% of Crohn's disease and ulcerative colitis subjects, respectively. Use of these concomitant therapies did not appear to influence the overall safety or efficacy of ustekinumab.

7.2 CYP450 Substrates

The formation of CYP450 enzymes can be suppressed by increased levels of certain cytokines (e.g., IL-1, IL-6, TNFα, IFN) during chronic inflammation. Thus, use of ustekinumab products, antagonists of IL-12 and IL-23, could normalize the formation of CYP450 enzymes. Upon initiation or discontinuation of WEZLANA in patients who are receiving concomitant CYP450 substrates, particularly those with a narrow therapeutic index, consider monitoring for therapeutic effect or drug concentration and adjust the individual dosage of the CYP substrate as needed. See the prescribing information of specific CYP substrates.

A CYP-mediated drug interaction effect was not observed in subjects with Crohn's disease [see Clinical Pharmacology (12.3)].

7.3 Allergen Immunotherapy

Ustekinumab products have not been evaluated in patients who have undergone allergy immunotherapy. Ustekinumab products may decrease the protective effect of allergen immunotherapy (decrease tolerance) which may increase the risk of an allergic reaction to a dose of allergen immunotherapy. Therefore, caution should be exercised in patients receiving or who have received allergen immunotherapy, particularly for anaphylaxis.

8 USE IN SPECIFIC POPULATIONS

8.1 Pregnancy

Risk Summary

Available data from the Organization of Teratology Information Specialists (OTIS)/MotherToBaby Pregnancy Registry, published literature and pharmacovigilance in pregnant women have not identified a ustekinumab-associated risk of major birth defects, miscarriage or other adverse maternal or fetal outcomes (see Data). There are risks to the mother and the fetus associated with inflammatory bowel disease (IBD) in pregnancy. In animal reproductive and developmental toxicity studies, no adverse developmental effects were observed in offspring after administration of ustekinumab to pregnant monkeys at exposures greater than 100 times the maximum recommended human dose (MRHD).

All pregnancies have a background risk of birth defect, loss, or other adverse outcomes. In the U.S. general population, the estimated background risk of major birth defects and miscarriage of clinically recognized pregnancies is 2% to 4% and 15% to 20%, respectively.

Clinical Considerations

Disease-associated Maternal and Embryo/Fetal Risk

Published data suggest that the risk of adverse pregnancy outcomes in women with IBD is associated with increased disease activity. Adverse pregnancy outcomes include preterm delivery (before 37 weeks of gestation), low birth weight (less than 2500 g) infants, and small for gestational age at birth.

Fetal/Neonatal Adverse Reactions

Transport of endogenous IgG antibodies across the placenta increases as pregnancy progresses, and peaks during the third trimester. Therefore, ustekinumab products may be present in infants exposed in utero. The potential clinical impact of ustekinumab product exposure in infants exposed in utero should be considered.

Data

Human Data

An observational pregnancy registry conducted by (OTIS)/MotherToBaby in the U.S. and Canada (enrollment between 2013 and 2019) assessed the risk of major birth defects, pattern of major and minor anomalies in live-born infants, miscarriage, and adverse infant outcomes in women with ustekinumab exposure. In the registry study, there were 101 participants and 107 pregnancies with exposure to ustekinumab (88 prospective; 19 retrospective). Most participants had a primary indication of CD (65.4%) or psoriasis (30.8%). The pregnancy registry did not identify a ustekinumab-associated risk of major birth defects, pattern of major or minor anomalies, increased risk of miscarriage or adverse infant outcomes. Methodological limitations of the registry include small sample size, lack of an internal comparison group, a mix of prospective and retrospective reports, and unmeasured confounders. The conclusions from the pregnancy registry were consistent with the published literature and pharmacovigilance.

Animal Data

Ustekinumab was tested in two embryo-fetal development toxicity studies in cynomolgus monkeys. No teratogenic or other adverse developmental effects were observed in fetuses from pregnant monkeys that were administered ustekinumab subcutaneously twice weekly or intravenously weekly during the period of organogenesis. Serum concentrations of ustekinumab in pregnant monkeys were greater than 100 times the serum concentration in patients treated subcutaneously with 90 mg of ustekinumab weekly for 4 weeks.

In a combined embryo-fetal development and pre- and post-natal development toxicity study, pregnant cynomolgus monkeys were administered subcutaneous doses of ustekinumab twice weekly at exposures greater than 100 times the MRHD from the beginning of organogenesis to Day 33 after delivery. Neonatal deaths occurred in the offspring of one monkey administered ustekinumab at 22.5 mg/kg and one monkey dosed at 45 mg/kg. No ustekinumab-related effects on functional, morphological, or immunological development were observed in the neonates from birth through six months of age.

8.2 Lactation

Risk Summary

Limited data from published literature suggests that ustekinumab is present in human breast milk. There are no available data on the effects of ustekinumab products on milk production. The effects of local gastrointestinal exposure and limited systemic exposure in the breastfed infant to ustekinumab products are unknown. No adverse effects on the breastfed infant causally related to ustekinumab products have been identified in the published literature or postmarketing experience.

The developmental and health benefits of breastfeeding should be considered along with the mother's clinical need for WEZLANA and any potential adverse effects on the breastfed child from WEZLANA or from the underlying maternal condition.

8.4 Pediatric Use

Plaque Psoriasis

The safety and effectiveness of WEZLANA have been established for the treatment of moderate to severe plaque psoriasis in pediatric patients 6 years of age and older who are candidates for phototherapy or systemic therapy.

Use of WEZLANA in pediatric patients 12 to less than 17 years of age is supported by evidence from a multicenter, randomized, 60-week trial (Ps STUDY 3) of ustekinumab that included a 12-week, double-blind, placebo-controlled, parallel-group portion, in 110 pediatric subjects 12 years of age and older [see Adverse Reactions (6.1), Clinical Studies (14.2)].

Use of WEZLANA in pediatric patients 6 to 11 years of age is supported by evidence from an open-label, single-arm, efficacy, safety, and pharmacokinetics trial (Ps STUDY 4) of ustekinumab in 44 subjects [see Adverse Reactions (6.1), Pharmacokinetics (12.3)].

The safety and effectiveness of WEZLANA have not been established in pediatric patients less than 6 years of age with plaque psoriasis.

Psoriatic Arthritis

The safety and effectiveness of WEZLANA have been established for treatment of psoriatic arthritis in pediatric patients 6 years of age and older.

Use of WEZLANA in these age groups is supported by evidence from adequate and well controlled trials of ustekinumab in adult subjects with psoriasis and PsA, pharmacokinetic data from adult subjects with psoriasis, adult subjects with PsA and pediatric subjects with psoriasis, and safety data of ustekinumab from two clinical trials in 44 pediatric subjects 6 to 11 years old with psoriasis and 110 pediatric subjects 12 years of age and older with psoriasis. The observed pre-dose (trough) concentrations are generally comparable between adult subjects with psoriasis, adult subjects with PsA and pediatric subjects with psoriasis, and the PK exposure is expected to be comparable between adult and pediatric subjects with PsA [see Adverse Reactions (6.1), Clinical Pharmacology (12.3), and Clinical Studies (14.1, 14.2, 14.3)].

The safety and effectiveness of WEZLANA have not been established in pediatric patients less than 6 years old with psoriatic arthritis.

Crohn's Disease and Ulcerative Colitis

The safety and effectiveness of WEZLANA have not been established in pediatric patients with Crohn's disease or ulcerative colitis.

8.5 Geriatric Use

Of the 6709 subjects exposed to ustekinumab, a total of 340 were 65 years of age or older (183 subjects with plaque psoriasis, 65 subjects with psoriatic arthritis, 58 subjects with Crohn's disease, and 34 subjects with ulcerative colitis), and 40 subjects were 75 years of age or older. Clinical trials of ustekinumab did not include sufficient numbers of subjects 65 years of age and older to determine whether they respond differently from younger adult subjects.

10 OVERDOSAGE

Single doses up to 6 mg/kg intravenously have been administered in clinical trials without dose-limiting toxicity. In case of overdosage, monitor the patient for any signs or symptoms of adverse reactions or effects and institute appropriate symptomatic treatment immediately. Consider contacting the Poison Help line 1-800-222-1222 or a medical toxicologist for additional overdose management recommendations.

11 DESCRIPTION

Ustekinumab-auub, a human IgG1κ monoclonal antibody, is a human interleukin -12 and -23 antagonist. Using DNA recombinant technology, ustekinumab-auub is produced in a mammalian cell line (Chinese Hamster Ovary). The manufacturing process contains steps for the clearance of viruses. Ustekinumab-auub is comprised of 1326 amino acids and has an estimated molecular mass that ranges from 148 to 150 kDa.

WEZLANA (ustekinumab-auub) injection is a sterile, preservative-free, clear to opalescent and colorless to light yellow solution with a pH of 6.0.

WEZLANA for Subcutaneous Use

Available as 45 mg of ustekinumab-auub in 0.5 mL and 90 mg of ustekinumab-auub in 1 mL, supplied as a sterile solution in a single-dose prefilled syringe with a 27 gauge fixed ½ inch needle and as 45 mg of ustekinumab-auub in 0.5 mL in a single-dose Type I glass vial with a coated stopper. The syringe is fitted with a passive needle guard and a needle cap that does not contain dry natural rubber (a derivative of latex).

Each 0.5 mL prefilled syringe or vial delivers 45 mg ustekinumab-auub, histidine (0.23 mg) and histidine hydrochloride monohydrate (0.36 mg), Polysorbate 80 (0.02 mg), and sucrose (38 mg).

Each 1 mL prefilled syringe delivers 90 mg ustekinumab-auub, histidine (0.46 mg) and histidine hydrochloride monohydrate (0.72 mg), Polysorbate 80 (0.04 mg), and sucrose (76 mg).

WEZLANA for Intravenous Infusion

Available as 130 mg of ustekinumab-auub in 26 mL, supplied as a single-dose Type I glass vial with a coated stopper.

Each 26 mL vial delivers 130 mg ustekinumab-auub, edetate disodium (0.47 mg), histidine (20 mg), histidine hydrochloride monohydrate (27 mg), methionine (10.4 mg), Polysorbate 80 (10.4 mg), and sucrose (2210 mg).

12 CLINICAL PHARMACOLOGY

12.1 Mechanism of Action

Ustekinumab products are human IgG1κ monoclonal antibodies that bind with specificity to the p40 protein subunit used by both the IL-12 and IL-23 cytokines. IL-12 and IL-23 are naturally occurring cytokines that are involved in inflammatory and immune responses, such as natural killer cell activation and CD4+ T -cell differentiation and activation. In in vitro models, ustekinumab products were shown to disrupt IL-12 and IL-23 mediated signaling and cytokine cascades by disrupting the interaction of these cytokines with a shared cell-surface receptor chain, IL-12Rβ1. The cytokines IL-12 and IL-23 have been implicated as important contributors to the chronic inflammation that is a hallmark of Crohn's disease and ulcerative colitis. In animal models of colitis, genetic absence or antibody blockade of the p40 subunit of IL-12 and IL-23, the target of ustekinumab products, was shown to be protective.

12.2 Pharmacodynamics

Plaque Psoriasis

In a small exploratory trial, a decrease was observed in the expression of mRNA of its molecular targets IL-12 and IL-23 in lesional skin biopsies measured at baseline and up to two weeks post-treatment in subjects with plaque psoriasis.

Ulcerative Colitis

In both trial UC-1 (induction) and trial UC-2 (maintenance), a positive relationship was observed between exposure and rates of clinical remission, clinical response, and endoscopic improvement. The response rate approached a plateau at the ustekinumab exposures associated with the recommended dosing regimen for maintenance treatment [see Clinical Studies (14.5)].

12.3 Pharmacokinetics

Absorption

In adult subjects with plaque psoriasis, the median time to reach the maximum serum concentration (Tmax) was 13.5 days and 7 days, respectively, after a single subcutaneous administration of 45 mg (N = 22) and 90 mg (N = 24) of ustekinumab. In healthy subjects (N = 30), the median Tmax value (8.5 days) following a single subcutaneous administration of 90 mg of ustekinumab was comparable to that observed in subjects with plaque psoriasis.

Following multiple subcutaneous doses of ustekinumab in adult subjects with plaque psoriasis, steady-state serum concentrations of ustekinumab were achieved by Week 28. The mean (±SD) steady-state trough serum ustekinumab concentrations were 0.69 ± 0.69 mcg/mL for subjects less than or equal to 100 kg receiving a 45 mg dose and 0.74 ± 0.78 mcg/mL for subjects greater than 100 kg receiving a 90 mg dose. There was no apparent accumulation in serum ustekinumab concentration over time when given subcutaneously every 12 weeks.

Following the recommended intravenous induction dose, mean ±SD peak serum ustekinumab concentration was 125.2 ± 33.6 mcg/mL in subjects with Crohn's disease, and 129.1 ± 27.6 mcg/mL in subjects with ulcerative colitis. Starting at Week 8, the recommended subcutaneous maintenance dosing of 90 mg ustekinumab was administered every 8 weeks. Steady-state ustekinumab concentration was achieved by the start of the second maintenance dose. There was no apparent accumulation in ustekinumab concentration over time when given subcutaneously every 8 weeks. Mean ±SD steady-state trough concentration was 2.5 ± 2.1 mcg/mL in subjects with Crohn's disease, and 3.3 ± 2.3 mcg/mL in subjects with ulcerative colitis for 90 mg ustekinumab administered every 8 weeks.

Distribution

Population pharmacokinetic analyses showed that the volume of distribution of ustekinumab in the central compartment was 2.7 L (95% CI: 2.69, 2.78) in subjects with Crohn's disease and 3.0 L (95% CI: 2.96, 3.07) in subjects with ulcerative colitis. The total volume of distribution at steady-state was 4.6 L in subjects with Crohn's disease and 4.4 L in subjects with ulcerative colitis.

Elimination

The mean (±SD) half-life ranged from 14.9 ± 4.6 to 45.6 ± 80.2 days across all trials in subjects with plaque psoriasis following subcutaneous administration. Population pharmacokinetic analyses showed that the clearance of ustekinumab was 0.19 L/day (95% CI: 0.185, 0.197) in subjects with Crohn's disease and 0.19 L/day (95% CI: 0.179, 0.192) in subjects with ulcerative colitis with an estimated median terminal half-life of approximately 19 days for both IBD (Crohn's disease and ulcerative colitis) populations.

These results indicate the pharmacokinetics of ustekinumab were similar between subjects with Crohn's disease and ulcerative colitis.

Metabolism

The metabolic pathway of ustekinumab products has not been characterized. As a human IgG1κ monoclonal antibody, ustekinumab products are expected to be degraded into small peptides and amino acids via catabolic pathways in the same manner as endogenous IgG.

Specific Populations

Weight

When given the same dose, subjects with plaque psoriasis or psoriatic arthritis weighing more than 100 kg had lower median serum ustekinumab concentrations compared with those subjects weighing 100 kg or less. The median trough serum concentrations of ustekinumab in subjects of higher weight (greater than 100 kg) in the 90 mg group were comparable to those in subjects of lower weight (100 kg or less) in the 45 mg group.

Age: Geriatric Population

A population pharmacokinetic analysis (N = 106/1937 subjects with plaque psoriasis greater than or equal to 65 years old) was performed to evaluate the effect of age on the pharmacokinetics of ustekinumab. There were no apparent changes in pharmacokinetic parameters (clearance and volume of distribution) in subjects older than 65 years old.

Age: Pediatric Population

Following multiple recommended doses of ustekinumab in pediatric subjects 6 years of age and older with plaque psoriasis, steady-state serum concentrations of ustekinumab were achieved by Week 28. At Week 28, the mean ±SD steady-state trough serum ustekinumab concentrations were 0.36 ± 0.26 mcg/mL and 0.54 ± 0.43 mcg/mL, respectively, in pediatric subjects 6 to 11 years of age and pediatric subjects 12 years of age and older.

Overall, the observed steady-state ustekinumab trough concentrations in pediatric subjects with plaque psoriasis were within the range of those observed for adult subjects with plaque psoriasis and adult subjects with PsA after administration of ustekinumab.

Drug Interaction Studies

The effects of IL-12 or IL-23 on the regulation of CYP450 enzymes were evaluated in an in vitro study using human hepatocytes, which showed that IL-12 and/or IL-23 at levels of 10 ng/mL did not alter human CYP450 enzyme activities (CYP1A2, 2B6, 2C9, 2C19, 2D6, or 3A4).

No clinically significant changes in exposure of caffeine (CYP1A2 substrate), warfarin (CYP2C9 substrate), omeprazole (CYP2C19 substrate), dextromethorphan (CYP2D6 substrate), or midazolam (CYP3A substrate) were observed when used concomitantly with ustekinumab at the approved recommended dosage in subjects with Crohn's disease [see Drug Interactions (7.2)].

Population pharmacokinetic analyses indicated that the clearance of ustekinumab was not impacted by concomitant MTX, NSAIDs, and oral corticosteroids, or prior exposure to a TNF blocker in subjects with psoriatic arthritis.

In subjects with Crohn's disease and ulcerative colitis, population pharmacokinetic analyses did not indicate changes in ustekinumab clearance with concomitant use of corticosteroids or immunomodulators (AZA, 6-MP, or MTX); and serum ustekinumab concentrations were not impacted by concomitant use of these medications.

13 NONCLINICAL TOXICOLOGY

13.1 Carcinogenesis, Mutagenesis, Impairment of Fertility

Animal studies have not been conducted to evaluate the carcinogenic or mutagenic potential of ustekinumab products. Published literature showed that administration of murine IL-12 caused an anti-tumor effect in mice that contained transplanted tumors and IL-12/IL-23p40 knockout mice or mice treated with anti-IL-12/IL-23p40 antibody had decreased host defense to tumors. Mice genetically manipulated to be deficient in both IL-12 and IL-23 or IL-12 alone developed UV-induced skin cancers earlier and more frequently compared to wild-type mice. The relevance of these experimental findings in mouse models for malignancy risk in humans is unknown.

No effects on fertility were observed in male cynomolgus monkeys that were administered ustekinumab at subcutaneous doses up to 45 mg/kg twice weekly (45 times the MRHD on a mg/kg basis) prior to and during the mating period. However, fertility and pregnancy outcomes were not evaluated in mated females.

No effects on fertility were observed in female mice that were administered an analogous IL-12/IL- 23p40 antibody by subcutaneous administration at doses up to 50 mg/kg, twice weekly, prior to and during early pregnancy.

13.2 Animal Toxicology and/or Pharmacology

In a 26-week toxicology study, one out of 10 monkeys subcutaneously administered 45 mg/kg ustekinumab twice weekly for 26 weeks had a bacterial infection.

14 CLINICAL STUDIES

14.1 Adult Subjects with Plaque Psoriasis

Two multicenter, randomized, double-blind, placebo-controlled trials (Ps STUDY 1 and Ps STUDY 2) enrolled a total of 1996 subjects 18 years of age and older with plaque psoriasis who had a minimum body surface area involvement of 10%, and Psoriasis Area and Severity Index (PASI) score ≥ 12, and who were candidates for phototherapy or systemic therapy. Subjects with guttate, erythrodermic, or pustular psoriasis were excluded from the trials.

Ps STUDY 1 enrolled 766 subjects and Ps STUDY 2 enrolled 1230 subjects. The trials had the same design through Week 28. In both trials, subjects were randomized in equal proportion to placebo, 45 mg or 90 mg of ustekinumab. Subjects randomized to ustekinumab received 45 mg or 90 mg doses, regardless of weight, at Weeks 0, 4, and 16. Subjects randomized to receive placebo at Weeks 0 and 4 crossed over to receive ustekinumab (either 45 mg or 90 mg) at Weeks 12 and 16.

In both trials, subjects in all treatment groups had a median baseline PASI score ranging from approximately 17 to 18. Baseline PGA score was marked or severe in 44% of subjects in Ps STUDY 1 and 40% of subjects in Ps STUDY 2. Approximately two-thirds of all subjects had received prior phototherapy, 69% had received either prior conventional systemic or biologic therapy for the treatment of psoriasis, with 56% receiving prior conventional systemic therapy and 43% receiving prior biologic therapy. A total of 28% of subjects had a history of psoriatic arthritis.

In both trials, the endpoints were the proportion of subjects who achieved at least a 75% reduction in PASI score (PASI 75) from baseline to Week 12 and treatment success (cleared or minimal) on the Physician's Global Assessment (PGA). The PGA is a 6-category scale ranging from 0 (cleared) to 5 (severe) that indicates the physician's overall assessment of psoriasis focusing on plaque thickness/induration, erythema, and scaling.

Clinical Response

The results of Ps STUDY 1 and Ps STUDY 2 are presented in Table 8 below.

Table 8. Clinical Outcomes at Week 12 in Adult Subjects with Plaque Psoriasis in Ps STUDY 1 and Ps STUDY 2
 | Ps STUDY 1 |  |  | Ps STUDY 2
 |  | ustekinumab |  |  | ustekinumab
 | Placebo | 45 mg | 90 mg | Placebo | 45 mg | 90 mg
Subjects randomized | 255 | 255 | 256 | 410 | 409 | 411
PASI 75 response | 8 (3%) | 171 (67%) | 170 (66%) | 15 (4%) | 273 (67 %) | 311 (76%)
PGA of Cleared or Minimal | 10 (4%) | 151 (59%) | 156 (61%) | 18 (4%) | 277 (68%) | 300 (73%)

Examination of age, gender, and race subgroups did not identify differences in response to ustekinumab among these subgroups.

In subjects who weighed 100 kg or less, response rates were comparable with both the 45 mg and 90 mg doses; however, in subjects who weighed greater than 100 kg, higher response rates were seen with 90 mg dosing compared with 45 mg dosing (Table 9 below).

Table 9. Clinical Outcomes by Weight at Week 12 in Adult Subjects with Plaque Psoriasis in Ps STUDY 1 and Ps STUDY 2
 | Ps STUDY 1 |  |  | Ps STUDY 2
 |  | ustekinumab |  |  | ustekinumab
 | Placebo | 45 mg | 90 mg | Placebo | 45 mg | 90 mg
Subjects randomized | 255 | 255 | 256 | 410 | 409 | 411
PASI 75 response [Subjects were dosed with trial medication at Weeks 0 and 4.]
≤ 100 kg | 4% | 74% | 65% | 4% | 73% | 78%
 | 6/166 | 124/168 | 107/164 | 12/290 | 218/297 | 225/289
> 100 kg | 2% | 54% | 68% | 3% | 49% | 71%
 | 2/89 | 47/87 | 63/92 | 3/120 | 55/112 | 86/121
PGA of Cleared or Minimal
≤ 100 kg | 4% | 64% | 63% | 5% | 74% | 75%
 | 7/166 | 108/168 | 103/164 | 14/290 | 220/297 | 216/289
> 100 kg | 3% | 49% | 58% | 3% | 51% | 69%
 | 3/89 | 43/87 | 53/92 | 4/120 | 57/112 | 84/121

Subjects in Ps STUDY 1 who were PASI 75 responders at both Weeks 28 and 40 were re-randomized at Week 40 to either continued dosing of ustekinumab (ustekinumab at Week 40) or to withdrawal of therapy (placebo at Week 40). At Week 52, 89% (144/162) of subjects re-randomized to ustekinumab treatment were PASI 75 responders compared with 63% (100/159) of subjects re-randomized to placebo (treatment withdrawal after Week 28 dose). The median time to loss of PASI 75 response among the subjects randomized to treatment withdrawal was 16 weeks.

14.2 Pediatric Subjects with Plaque Psoriasis

A multicenter, randomized, double blind, placebo-controlled trial (Ps STUDY 3) enrolled 110 pediatric subjects 12 years of age and older with a minimum BSA involvement of 10%, a PASI score greater than or equal to 12, and a PGA score greater than or equal to 3, who were candidates for phototherapy or systemic therapy and whose disease was inadequately controlled by topical therapy.

Subjects were randomized to receive placebo (n = 37), the recommended dose of ustekinumab (n = 36), or one -half the recommended dose of ustekinumab (n = 37) by subcutaneous injection at Weeks 0 and 4 followed by dosing every 12 weeks (q12w). The recommended dose of ustekinumab was 0.75 mg/kg for subjects weighing less than 60 kg, 45 mg for subjects weighing 60 kg to 100 kg, and 90 mg for subjects weighing greater than 100 kg. At Week 12, subjects who received placebo were crossed over to receive ustekinumab at the recommended dose or one -half the recommended dose.

Of the pediatric subjects, approximately 63% had prior exposure to phototherapy or conventional systemic therapy and approximately 11% had prior exposure to biologics.

The endpoints were the proportion of subjects who achieved a PGA score of cleared (0) or minimal (1), PASI 75, and PASI 90 at Week 12. Subjects were followed for up to 60 weeks following first administration of trial agent.

Clinical Response

The efficacy results at Week 12 for Ps STUDY 3 are presented in Table 10.

Table 10. Efficacy Results at Week 12 in Pediatric Subjects 12 Years of Age and Older with Plaque Psoriasis in Ps STUDY 3
 | Ps STUDY 3
 | Placebo n (%) | ustekinumab [Using the weight-based dosage regimen specified in Table 1 and Table 2.] n (%)
N | 37 | 36
PGA
PGA of cleared (0) or minimal (1) | 2 (5.4%) | 25 (69.4%)
PASI
PASI 75 responders | 4 (10.8%) | 29 (80.6%)
PASI 90 responders | 2 (5.4%) | 22 (61.1%)

14.3 Psoriatic Arthritis

The safety and efficacy of ustekinumab was assessed in 927 subjects (PsA STUDY 1, n = 615; PsA STUDY 2, n = 312), in two randomized, double-blind, placebo-controlled trials in adult subjects 18 years of age and older with active PsA (≥ 5 swollen joints and ≥ 5 tender joints) despite non-steroidal anti-inflammatory (NSAID) or disease modifying antirheumatic (DMARD) therapy. Subjects in these trials had a diagnosis of PsA for at least 6 months. Subjects with each subtype of PsA were enrolled, including polyarticular arthritis with the absence of rheumatoid nodules (39%), spondylitis with peripheral arthritis (28%), asymmetric peripheral arthritis (21%), distal interphalangeal involvement (12%) and arthritis mutilans (0.5%). Over 70% and 40% of the patients, respectively, had enthesitis and dactylitis at baseline.

Subjects were randomized to receive treatment with ustekinumab 45 mg, 90 mg, or placebo subcutaneously at Weeks 0 and 4 followed by every 12 weeks (q12w) dosing. Approximately 50% of subjects continued on stable doses of MTX (≤ 25 mg/week). The primary endpoint was the percentage of subjects achieving ACR 20 response at Week 24. In PsA STUDY 1 and PsA STUDY 2, 80% and 86% of the subjects, respectively, had been previously treated with DMARDs. In PsA STUDY 1, previous treatment with anti-tumor necrosis factor (TNF)-α agent was not allowed. In PsA STUDY 2, 58% (n = 180) of the subjects had been previously treated with TNF blocker, of whom over 70% had discontinued their TNF blocker treatment for lack of efficacy or intolerance at any time.

Clinical Response

In both trials, a greater proportion of subjects achieved ACR 20, ACR 50 and PASI 75 response in the ustekinumab 45 mg and 90 mg groups compared to placebo at Week 24 (see Table 11). ACR 70 responses were also higher in the ustekinumab 45 mg and 90 mg groups, although the difference was only numerical (p = NS) in STUDY 2. Responses were consistent in subjects treated with ustekinumab alone or in combination with methotrexate. Responses were similar in subjects regardless of prior TNFα exposure.

Table 11. ACR 20, ACR 50, ACR 70 and PASI 75 Responses in PsA STUDY 1 and PsA STUDY 2 at Week 24
 | PsA STUDY 1 |  |  | PsA STUDY 2
 | ustekinumab |  |  | ustekinumab
 | Placebo | 45 mg | 90 mg | Placebo | 45 mg | 90 mg
Number of subjects randomized | 206 | 205 | 204 | 104 | 103 | 105
ACR 20 response, N (%) | 47 (23%) | 87 (42%) | 101 (50%) | 21 (20%) | 45 (44%) | 46 (44%)
ACR 50 response, N (%) | 18 (9%) | 51 (25%) | 57 (28%) | 7 (7%) | 18 (17%) | 24 (23%)
ACR 70 response, N (%) | 5 (2%) | 25 (12%) | 29 (14%) | 3 (3%) | 7 (7%) | 9 (9%)
Number of subjects with ≥ 3% BSA [Number of subjects with ≥ 3% BSA psoriasis skin involvement at baseline.] | 146 | 145 | 149 | 80 | 80 | 81
PASI 75 response, N (%) | 16 (11%) | 83 (57%) | 93 (62%) | 4 (5%) | 41 (51%) | 45 (56%)

The percent of subjects achieving ACR 20 responses by visit is shown in Figure 1.

Figure 1. Percent of subjects achieving ACR 20 response through Week 24

The results of the components of the ACR response criteria are shown in Table 12.

Table 12. Mean Change from Baseline in ACR Components at Week 24
 |  | PsA STUDY 1
 | Placebo | ustekinumab
 | (N = 206) | 45 mg (N = 205) | 90 mg (N = 204)
Number of swollen joints [Number of swollen joints counted (0–66).]
Baseline | 15 | 12 | 13
Mean Change at Week 24 | -3 | -5 | -6
Number of tender joints [Number of tender joints counted (0–68).]
Baseline | 25 | 22 | 23
Mean Change at Week 24 | -4 | -8 | -9
Subjects' assessment of pain [Visual analogue scale; 0 = best, 10 = worst.]
Baseline | 6.1 | 6.2 | 6.6
Mean Change at Week 24 | -0.5 | -2.0 | -2.6
Subject global assessment
Baseline | 6.1 | 6.3 | 6.4
Mean Change at Week 24 | -0.5 | -2.0 | -2.5
Physician global assessment
Baseline | 5.8 | 5.7 | 6.1
Mean Change at Week 24 | -1.4 | -2.6 | -3.1
Disability index (HAQ) [Disability Index of the Health Assessment Questionnaire; 0 = best, 3 = worst, measures the patient's ability to perform the following: dress/groom, arise, eat, walk, reach, grip, maintain hygiene, and maintain daily activity.]
Baseline | 1.2 | 1.2 | 1.2
Mean Change at Week 24 | -0.1 | -0.3 | -0.4
CRP (mg/dL) [CRP: (Normal Range 0.0–1.0 mg/dL).]
Baseline | 1.6 | 1.7 | 1.8
Mean Change at Week 24 | 0.01 | -0.5 | -0.8

An improvement in enthesitis and dactylitis scores was observed in each ustekinumab group compared with placebo at Week 24.

Physical Function

Ustekinumab-treated subjects showed improvement in physical function compared to subjects receiving placebo as assessed by HAQ-DI at Week 24. In both trials, the proportion of HAQ-DI responders (≥ 0.3 improvement in HAQ-DI score) was greater in the ustekinumab 45 mg and 90 mg groups compared to placebo at Week 24.

14.4 Crohn's Disease

Ustekinumab was evaluated in three randomized, double-blind, placebo-controlled clinical trials in adult subjects with moderately to severely active Crohn's disease (Crohn's Disease Activity Index [CDAI] score of 220 to 450). There were two 8-week intravenous induction trials (CD-1 and CD-2) followed by a 44-week subcutaneous randomized withdrawal maintenance trial (CD-3) representing 52 weeks of therapy. Subjects in CD-1 had failed or were intolerant to treatment with one or more TNF blockers, while subjects in CD-2 had failed or were intolerant to treatment with immunomodulators or corticosteroids, but never failed treatment with a TNF blocker.

Trials CD-1 and CD-2

In trials CD-1 and CD-2, 1409 subjects were randomized, of whom 1368 (CD-1, n = 741; CD-2, n = 627) were included in the final efficacy analysis. Induction of clinical response (defined as a reduction in CDAI score of greater than or equal to 100 points or CDAI score of less than 150) at Week 6 and clinical remission (defined as a CDAI score of less than 150) at Week 8 were evaluated. In both trials, subjects were randomized to receive a single intravenous administration of ustekinumab at either approximately 6 mg/kg, placebo (see Table 4), or 130 mg (a lower dose than recommended).

In trial CD-1, subjects had failed or were intolerant to prior treatment with a TNF blocker: 29% subjects had an inadequate initial response (primary non-responders), 69% responded but subsequently lost response (secondary non-responders) and 36% were intolerant to a TNF blocker. Of these subjects, 48% failed or were intolerant to one TNF blocker and 52% had failed 2 or 3 prior TNF blockers. At baseline and throughout the trial, approximately 46% of the subjects were receiving corticosteroids and 31% of the subjects were receiving immunomodulators (AZA, 6-MP, MTX). The median baseline CDAI score was 319 in the ustekinumab approximately 6 mg/kg group and 313 in the placebo group.

In trial CD-2, subjects had failed or were intolerant to prior treatment with corticosteroids (81% of subjects), at least one immunomodulator (6-MP, AZA, MTX; 68% of subjects), or both (49% of subjects). Additionally, 69% never received a TNF blocker and 31% previously received but had not failed a TNF blocker. At baseline, and throughout the trial, approximately 39% of the subjects were receiving corticosteroids and 35% of the subjects were receiving immunomodulators (AZA, 6-MP, MTX). The median baseline CDAI score was 286 in the ustekinumab and 290 in the placebo group.

In these induction trials, a greater proportion of subjects treated with ustekinumab (at the recommended dose of approximately 6 mg/kg dose) achieved clinical response at Week 6 and clinical remission at Week 8 compared to placebo (see Table 13 for clinical response and remission rates).

Clinical response and remission were significant as early as Week 3 in ustekinumab-treated subjects and continued to improve through Week 8.

Table 13. Induction of Clinical Response and Remission in CD-1 [Patient population consisted of subjects who failed or were intolerant to TNF blocker therapy.] and CD-2 [Patient population consisted of subjects who failed or were intolerant to corticosteroids or immunomodulators (e.g., 6-MP, AZA, MTX) and previously received but not failed a TNF blocker or were never treated with a TNF blocker.]
 | CD-1 n = 741 |  |  | CD-2 n = 627
 | Placebo N = 247 | Ustekinumab [Infusion dose of ustekinumab using the weight-based dosage regimen specified in Table 4.] N = 249 | Treatment difference and 95% CI | Placebo N = 209 | Ustekinumab N = 209 | Treatment difference and 95% CI
Clinical Response (100 point), Week 6 | 53 (21%) | 84 (34%) [0.001 ≤ p < 0.01.] | 12% (4%, 20%) | 60 (29%) | 116 (56%) [p < 0.001.] | 27% (18%, 36%)
Clinical Remission, Week 8 | 18 (7%) | 52 (21%) | 14% (8%, 20%) | 41 (20%) | 84 (40%) | 21% (12%, 29%)
Clinical Response (100 point), Week 8 | 50 (20%) | 94 (38%) | 18% (10%, 25%) | 67 (32%) | 121 (58%) | 26% (17%, 35%)
70 Point Response, Week 6 | 75 (30%) | 109 (44%) | 13% (5%, 22%) | 81 (39%) | 135 (65%) | 26% (17%, 35%)
70 Point Response, Week 3 | 67 (27%) | 101 (41%) | 13% (5%, 22%) | 66 (32%) | 106 (51%) | 19% (10%, 28%)
Clinical remission is defined as CDAI score < 150; Clinical response is defined as reduction in CDAI score by at least 100 points or being in clinical remission: 70 point response is defined as reduction in CDAI score by at least 70 points

Trial CD-3

The maintenance trial (CD-3) evaluated 388 subjects who achieved clinical response (≥ 100 point reduction in CDAI score) at Week 8 with either induction dose of ustekinumab in trials CD-1 or CD-2. Subjects were randomized to receive a subcutaneous maintenance regimen of either 90 mg ustekinumab every 8 weeks or placebo for 44 weeks (see Table 14).

Table 14. Clinical Response and Remission in CD-3 (Week 44; 52 weeks from initiation of the induction dose)
 | Placebo [The placebo group consisted of subjects who were in response to ustekinumab and were randomized to receive placebo at the start of maintenance therapy.] N = 131 [Subjects who achieved clinical response to ustekinumab at the end of the induction trial.] | 90 mg ustekinumab every 8 weeks N = 128 | Treatment difference and 95% CI
Clinical Remission | 47 (36%) | 68 (53%) [p < 0.01.] | 17% (5%,29%)
Clinical Response | 58 (44%) | 76 (59%) [0.01≤ p < 0.05.] | 15% (3%,27%)
Clinical Remission in patients in remission at the start of maintenance therapy [Subjects in remission at the end of maintenance therapy who were in remission at the start of maintenance therapy. This does not account for any other time point during maintenance therapy.] | 36/79 (46%) | 52/78 (67%) | 21% (6%, 36%)
Clinical remission is defined as CDAI score < 150; Clinical response is defined as reduction in CDAI of at least 100 points or being in clinical remission

At Week 44, 47% of subjects who received ustekinumab were corticosteroid-free and in clinical remission, compared to 30% of subjects in the placebo group.

At Week 0 of trial CD-3, 34/56 (61%) ustekinumab-treated subjects who previously failed or were intolerant to TNF blocker therapies were in clinical remission and 23/56 (41%) of these subjects were in clinical remission at Week 44. In the placebo arm, 27/61 (44%) subjects were in clinical remission at Week 0 while 16/61 (26%) of these subjects were in remission at Week 44.

At Week 0 of trial CD-3, 46/72 (64%) ustekinumab-treated subjects who had previously failed immunomodulator therapy or corticosteroids (but not TNF blockers) were in clinical remission and 45/72 (63%) of these subjects were in clinical remission at Week 44. In the placebo arm, 50/70 (71%) of these subjects were in clinical remission at Week 0 while 31/70 (44%) were in remission at Week 44. In the subset of these subjects who were also naïve to TNF blockers, 34/52 (65%) of ustekinumab-treated subjects were in clinical remission at Week 44 as compared to 25/51 (49%) in the placebo arm.

Subjects who were not in clinical response 8 weeks after ustekinumab induction were not included in the primary efficacy analyses for trial CD-3; however, these subjects were eligible to receive a 90 mg subcutaneous injection of ustekinumab upon entry into trial CD-3. Of these subjects, 102/219 (47%) achieved clinical response eight weeks later and were followed for the duration of the trial.

14.5 Ulcerative Colitis

Ustekinumab was evaluated in two randomized, double-blind, placebo-controlled clinical trials [UC-1 and UC-2 (NCT02407236)] in adult subjects with moderately to severely active ulcerative colitis who had an inadequate response to or failed to tolerate a biologic (i.e., TNF blocker and/or vedolizumab), corticosteroids, and/or 6-MP or AZA therapy. The 8-week intravenous induction trial (UC-1) was followed by the 44-week subcutaneous randomized withdrawal maintenance trial (UC-2) for a total of 52 weeks of therapy.

Disease assessment was based on the Mayo score, which ranged from 0 to 12 and has four subscores that were each scored from 0 (normal) to 3 (most severe): stool frequency, rectal bleeding, findings on centrally- reviewed endoscopy, and physician global assessment. Moderately to severely active ulcerative colitis was defined at baseline (Week 0) as Mayo score of 6 to 12, including a Mayo endoscopy subscore ≥ 2. An endoscopy score of 2 was defined by marked erythema, absent vascular pattern, friability, erosions; and a score of 3 was defined by spontaneous bleeding, ulceration. At baseline, subjects had a median Mayo score of 9, with 84% of subjects having moderate disease (Mayo score 6–10) and 15% having severe disease (Mayo score 11–12).

Subjects in these trials may have received other concomitant therapies including aminosalicylates, immunomodulatory agents (AZA, 6-MP, or MTX), and oral corticosteroids (prednisone).

Trial UC-1

In UC-1, 961 subjects were randomized at Week 0 to a single intravenous administration of ustekinumab of approximately 6 mg/kg, 130 mg (a lower dose than recommended), or placebo. Subjects enrolled in UC-1 had to have failed therapy with corticosteroids, immunomodulators or at least one biologic. A total of 51% had failed at least one biologic and 17% had failed both a TNF blocker and an integrin receptor blocker. Of the total population, 46% had failed corticosteroids or immunomodulators but were biologic-naïve and an additional 3% had previously received but had not failed a biologic. At induction baseline and throughout the trial, approximately 52% subjects were receiving oral corticosteroids, 28% subjects were receiving immunomodulators (AZA, 6-MP, or MTX) and 69% subjects were receiving aminosalicylates.

The primary endpoint was clinical remission at Week 8. Clinical remission with a definition of: Mayo stool frequency subscore of 0 or 1, Mayo rectal bleeding subscore of 0 (no rectal bleeding), and Mayo endoscopy subscore of 0 or 1 (Mayo endoscopy subscore of 0 defined as normal or inactive disease and Mayo subscore of 1 defined as presence of erythema, decreased vascular pattern and no friability) is provided in Table 15.

The secondary endpoints were clinical response, endoscopic improvement, and histologic-endoscopic mucosal improvement. Clinical response with a definition of (≥ 2 points and ≥ 30% decrease in modified Mayo score, defined as 3-component Mayo score without the Physician's Global Assessment, with either a decrease from baseline in the rectal bleeding subscore ≥ 1 or a rectal bleeding subscore of 0 or 1), endoscopic improvement with a definition of Mayo endoscopy subscore of 0 or 1, and histologic-endoscopic mucosal improvement with a definition of combined endoscopic improvement and histologic improvement of the colon tissue [neutrophil infiltration in < 5% of crypts, no crypt destruction, and no erosions, ulcerations, or granulation tissue] are provided in Table 15.

In UC-1, a significantly greater proportion of subjects treated with ustekinumab (at the recommended dose of approximately 6 mg/kg dose) were in clinical remission and response and achieved endoscopic improvement and histologic-endoscopic mucosal improvement compared to placebo (see Table 15).

Table 15. Proportion of Subjects Meeting Efficacy Endpoints at Week 8 in UC-1
Endpoint | Placebo N = 319 |  | Ustekinumab [Infusion dose of ustekinumab using the weight- based dosage regimen specified in Table 4.] N = 322 |  | Treatment difference and 97.5% CI [Adjusted treatment difference (97.5% CI).]
Endpoint | N | % | N | % | Treatment difference and 97.5% CI [Adjusted treatment difference (97.5% CI).]
Clinical Remission [Clinical remission was defined as Mayo stool frequency subscore of 0 or 1, Mayo rectal bleeding subscore of 0, and Mayo endoscopy subscore of 0 or 1 (modified so that 1 does not include friability).] | 22 | 7% | 62 | 19% | 12% (7%, 18%) [p < 0.001.]
Bio-naïve [An additional 7 subjects on placebo and 9 subjects on ustekinumab (6 mg/kg) had been exposed to, but had not failed, biologics.] | 14/151 | 9% | 36/147 | 24%
Prior biologic failure | 7/161 | 4% | 24/166 | 14%
Endoscopic Improvement [Endoscopic improvement was defined as Mayo endoscopy subscore of 0 or 1 (modified so that 1 does not include friability).] | 40 | 13% | 80 | 25% | 12% (6%, 19%)
Bio-naïve | 28/151 | 19% | 43/147 | 29%
Prior biologic failure | 11/161 | 7% | 34/166 | 20%
Clinical Response [Clinical response was defined as a decrease from baseline in the modified Mayo score by ≥ 30% and ≥ 2 points, with either a decrease from baseline in the rectal bleeding subscore ≥ 1 or a rectal bleeding subscore of 0 or 1.] | 99 | 31% | 186 | 58% | 27% (18%, 35%)
Bio-naïve | 55/151 | 36% | 94/147 | 64%
Prior biologic failure | 42/161 | 26% | 86/166 | 52%
Histologic-Endoscopic Mucosal Improvement [Histologic-endoscopic mucosal improvement was defined as combined endoscopic improvement (Mayo endoscopy subscore of 0 or 1) and histologic improvement of the colon tissue (neutrophil infiltration in < 5% of crypts, no crypt destruction, and no erosions, ulcerations, or granulation tissue).] | 26 | 8% | 54 | 17% | 9% (3%, 14%)
Bio-naïve | 19/151 | 13% | 30/147 | 20%
Prior biologic failure | 6/161 | 4% | 21/166 | 13%

The relationship of histologic-endoscopic mucosal improvement, as defined in UC-1, at Week 8 to disease progression and long-term outcomes was not evaluated during UC-1.

Rectal Bleeding and Stool Frequency Subscores

Decreases in rectal bleeding and stool frequency subscores were observed as early as Week 2 in ustekinumab-treated subjects.

Trial UC-2

The maintenance trial (UC-2) evaluated 523 subjects who achieved clinical response 8 weeks following the intravenous administration of either induction dose of ustekinumab in UC-1. These subjects were randomized to receive a subcutaneous maintenance regimen of either 90 mg ustekinumab every 8 weeks, or every 12 weeks (a lower dose than recommended), or placebo for 44 weeks.

The primary endpoint was the proportion of subjects in clinical remission at Week 44. The secondary endpoints included the proportion of subjects maintaining clinical response at Week 44, the proportion of subjects with endoscopic improvement at Week 44, the proportion of subjects with corticosteroid-free clinical remission at Week 44, and the proportion of subjects maintaining clinical remission at Week 44 among subjects who achieved clinical remission 8 weeks after induction.

Results of the primary and secondary endpoints at Week 44 in subjects treated with ustekinumab at the recommended dosage (90 mg every 8 weeks) compared to the placebo are shown in Table 16.

Table 16. Efficacy Endpoints of Maintenance at Week 44 in UC-2 (52 Weeks from Initiation of the Induction Dose)
Endpoint | Placebo [The placebo group consisted of subjects who were in response to ustekinumab and were randomized to receive placebo at the start of maintenance therapy.] N = 175 [Clinical response was defined as a decrease from baseline in the modified Mayo score by ≥ 30% and ≥ 2 points, with either a decrease from baseline in the rectal bleeding subscore ≥ 1 or a rectal bleeding subscore of 0 or 1.] |  | 90 mg ustekinumab every 8 weeks N = 176 |  | Treatment difference and 95% CI
Endpoint | N | % | N | % | Treatment difference and 95% CI
Clinical Remission [Clinical remission was defined as Mayo stool frequency subscore of 0 or 1, Mayo rectal bleeding subscore of 0, and Mayo endoscopy subscore of 0 or 1 (modified so that 1 does not include friability).] | 46 | 26% | 79 | 45% | 19% (9%, 28%) [p = < 0.001.]
Bio-naïve [An additional 3 subjects on placebo and 6 patients on ustekinumab had been exposed to, but had not failed, biologics.] | 30/84 | 36% | 39/79 | 49%
Prior biologic failure | 16/88 | 18% | 37/91 | 41%
Maintenance of Clinical Response at Week 44 | 84 | 48% | 130 | 74% | 26% (16%, 36%)
Bio-naïve | 49/84 | 58% | 62/79 | 78%
Prior biologic failure | 35/88 | 40% | 64/91 | 70%
Endoscopic Improvement [Endoscopic improvement was defined as Mayo endoscopy subscore of 0 or 1 (modified so that 1 does not include friability).] | 47 | 27% | 83 | 47% | 20% (11%, 30%)
Bio-naïve | 29/84 | 35% | 42/79 | 53%
Prior biologic failure | 18/88 | 20% | 38/91 | 42%
Corticosteroid-free Clinical Remission [Corticosteroid-free clinical remission was defined as subjects in clinical remission and not receiving corticosteroids at Week 44.] | 45 | 26% | 76 | 43% | 17% (8%, 27%)
Bio-naïve | 30/84 | 36% | 38/79 | 48%
Prior biologic failure | 15/88 | 17% | 35/91 | 38%
Maintenance of Clinical Remission at Week 44 in subjects who achieved clinical remission 8 weeks after induction | 18/50 | 36% | 27/41 | 66% | 31% (12%, 50%) [p = 0.004.]
Bio-naïve | 12/27 | 44% | 14/20 | 70%
Prior biologic failure | 6/23 | 26% | 12/18 | 67%

Other Endpoints

Week 16 Responders to Ustekinumab Induction

Subjects who were not in clinical response 8 weeks after induction with ustekinumab in UC-1 were not included in the primary efficacy analyses for trial UC-2; however, these subjects were eligible to receive a 90 mg subcutaneous injection of ustekinumab at Week 8. Of these subjects, 55/101 (54%) achieved clinical response eight weeks later (Week 16) and received ustekinumab 90 mg subcutaneously every 8 weeks during the UC-2 trial. At Week 44, there were 97/157 (62%) subjects who maintained clinical response and there were 51/157 (32%) who achieved clinical remission.

Histologic-Endoscopic Mucosal Improvement at Week 44

The proportion of subjects achieving histologic-endoscopic mucosal improvement during maintenance treatment in UC-2 was 75/172 (44%) among subjects on ustekinumab and 40/172 (23%) in subjects on placebo at Week 44. The relationship of histologic-endoscopic mucosal improvement, as defined in UC-2, at Week 44 to progression of disease or long-term outcomes was not evaluated in UC-2.

Endoscopic Normalization

Normalization of endoscopic appearance of the mucosa was defined as a Mayo endoscopic subscore of 0. At Week 8 in UC-1, endoscopic normalization was achieved in 25/322 (8%) of subjects treated with ustekinumab and 12/319 (4%) of subjects in the placebo group. At Week 44 of UC-2, endoscopic normalization was achieved in 51/176 (29%) of subjects treated with ustekinumab and in 32/175 (18%) of subjects in placebo group.

15 REFERENCES

1 Surveillance, Epidemiology, and End Results (SEER) Program (www.seer.cancer.gov) SEER*Stat Database: Incidence - SEER 6.6.2 Regs Research Data, Nov 2009 Sub (1973–2007) – Linked To County Attributes - Total U.S., 1969–2007 Counties, National Cancer Institute, DCCPS, Surveillance Research Program, Surveillance Systems Branch, released April 2010, based on the November 2009 submission.

16 HOW SUPPLIED/STORAGE AND HANDLING

WEZLANA (ustekinumab-auub) injection is a sterile, preservative-free, clear to opalescent and colorless to light yellow solution. It is supplied as individually packaged, single-dose prefilled syringes or single-dose vials.

For Subcutaneous Use

Prefilled Syringes

- 45 mg/0.5 mL (NDC 84612-076-01, NDC 84612-876-01)
- 90 mg/mL (NDC 84612-089-01, NDC 84612-889-01)

Each prefilled syringe is equipped with a 27-gauge fixed ½ inch needle, a needle safety guard, and a needle cover that does not contain dry natural rubber.

Single-dose Vial

- 45 mg/0.5 mL (NDC 84612-055-01, NDC 84612-855-01)

For Intravenous Infusion

Single-dose Vial

- 130 mg/26 mL (5 mg/mL) (NDC 84612-066-01)

Storage and Stability

Store WEZLANA vials and prefilled syringes refrigerated between 2°C to 8°C (36°F to 46°F). Keep the product in the original carton to protect from light until the time of use. Do not freeze. Do not shake.

If needed, individual prefilled syringe and 45 mg vial may be stored at room temperature up to 30°C (86°F) for a maximum single period of up to 30 days in the original carton to protect from light. Record the date when the prefilled syringe or the 45 mg vial is first removed from the refrigerator on the carton in the space provided. Once the prefilled syringe or the 45 mg vial has been stored at room temperature, do not return it to the refrigerator.

Discard the prefilled syringe or the 45 mg vial if not used within 30 days at room temperature storage. Do not use WEZLANA after the expiration date on the carton or on the prefilled syringe or on the 45 mg vial.

17 PATIENT COUNSELING INFORMATION

Advise the patient and/or caregiver to read the FDA-approved patient labeling (Medication Guide and Instructions for Use).

Infections

Inform patients that WEZLANA may lower the ability of their immune system to fight infections and to contact their healthcare provider immediately if they develop any signs or symptoms of infection [see Warnings and Precautions (5.1)].

Malignancies

Inform patients of the risk of developing malignancies while receiving WEZLANA [see Warnings and Precautions (5.4)].

Hypersensitivity Reactions

- Advise patients to seek immediate medical attention if they experience any signs or symptoms of serious hypersensitivity reactions and discontinue WEZLANA [see Warnings and Precautions (5.5)].

Posterior Reversible Encephalopathy Syndrome (PRES)

Inform patients to immediately contact their healthcare provider if they experience signs and symptoms of PRES (which may include headache, seizures, confusion, or visual disturbances) [see Warnings and Precautions (5.6)].

Immunizations

Inform patients that WEZLANA can interfere with the usual response to immunizations and that they should avoid live vaccines [see Warnings and Precautions (5.7)].

Administration

Instruct patients to follow sharps disposal recommendations, as described in the Instructions for Use.

WEZLANA™ (ustekinumab-auub)

Manufactured for Nuvaila, Dublin, Ireland

Manufactured by:
Amgen Inc.,
One Amgen Center Drive,
Thousand Oaks, CA 91320-1799

U.S. License Number 1080

WEZLANA™ (ustekinumab-auub) is a trademark owned or licensed by Amgen Inc., its subsidiaries, or affiliates.
All third party trademarks are the property of their respective owners.

© 2025 Amgen Inc. All rights reserved.

1xxxxxx-v3

MEDICATION GUIDE
WEZLANA™ (wez-LAH-nah)
(ustekinumab-auub)
injection, for subcutaneous or intravenous use

What is the most important information I should know about WEZLANA?
WEZLANA is a medicine that affects your immune system. WEZLANA can increase your risk of having serious side effects, including:

- Serious infections. WEZLANA may lower the ability of your immune system to fight infections and may increase your risk of infections. Some people have serious infections during treatment with ustekinumab products, including tuberculosis (TB), and infections caused by bacteria, fungi, or viruses. Some people have to be hospitalized for treatment of their infection.

- Your healthcare provider should check you for TB before starting WEZLANA.
- If your healthcare provider feels that you are at risk for TB, you may be treated with medicine for TB before you begin treatment with WEZLANA and during treatment with WEZLANA.
- Your healthcare provider should watch you closely for signs and symptoms of TB while you are being treated with WEZLANA.

You should not start WEZLANA if you have any kind of infection unless your healthcare provider says it is okay.
Before starting WEZLANA, tell your healthcare provider if you:

- think you have an infection or have symptoms of an infection such as:

- fever, sweat, or chills
- muscle aches
- cough
- shortness of breath
- blood in phlegm

- weight loss
- warm, red, or painful skin or sores on your body
- diarrhea or stomach pain
- burning when you urinate or urinate more often than normal
- feel very tired

- are being treated for an infection or have any open cuts.
- get a lot of infections or have infections that keep coming back.
- have TB or have been in close contact with someone with TB.

After starting WEZLANA, call your healthcare provider right away if you have any symptoms of an infection (see above). These may be signs of infections such as chest infections, or skin infections or shingles that could have serious complications. WEZLANA can make you more likely to get infections or make an infection that you have worse.

- People who have a genetic problem where the body does not make any of the proteins interleukin 12 (IL-12) and interleukin 23 (IL-23) are at a higher risk for certain serious infections. These infections can spread throughout the body and cause death. People who take WEZLANA may also be more likely to get these infections.
- Cancers. WEZLANA may decrease the activity of your immune system and increase your risk for certain types of cancers. Tell your healthcare provider if you have ever had any type of cancer. Some people who are receiving ustekinumab products and have risk factors for skin cancer have developed certain types of skin cancers. During your treatment with WEZLANA, tell your healthcare provider if you develop any new skin growths.

What is WEZLANA?
WEZLANA is a prescription medicine used to treat:

- adults and children 6 years of age and older with moderate to severe plaque psoriasis who may benefit from taking injections or pills (systemic therapy) or phototherapy (treatment using ultraviolet light alone or with pills).
- adults and children 6 years of age and older with active psoriatic arthritis.
- adults with moderately to severely active Crohn's disease.
- adults with moderately to severely active ulcerative colitis.

It is not known if WEZLANA is safe and effective in children with Crohn's disease or ulcerative colitis or in children less than 6 years of age with plaque psoriasis or psoriatic arthritis.

Who should not use WEZLANA?
Do not use WEZLANA if you are allergic to ustekinumab products or any of the ingredients in WEZLANA. See the end of this Medication Guide for a complete list of ingredients in WEZLANA.

Before you use or receive WEZLANA, tell your healthcare provider about all of your medical conditions, including if you:

- have any of the conditions or symptoms listed in the section "What is the most important information I should know about WEZLANA?"
- ever had an allergic reaction to ustekinumab products. Ask your healthcare provider if you are not sure.
- have recently received or are scheduled to receive an immunization (vaccine). People who are being treated with WEZLANA should avoid receiving live vaccines. Tell your healthcare provider if anyone in your house needs a live vaccine. The viruses used in some types of live vaccines can spread to people with a weakened immune system and can cause serious problems. You should avoid receiving the BCG vaccine during the one year before receiving WEZLANA or one year after you stop receiving WEZLANA.
- have any new or changing lesions within psoriasis areas or on normal skin.
- are receiving or have received allergy shots, especially for serious allergic reactions. Allergy shots may not work as well for you during treatment with WEZLANA. WEZLANA may also increase your risk of having an allergic reaction to an allergy shot.
- receive or have received phototherapy for your psoriasis.
- are pregnant or plan to become pregnant. It is not known if WEZLANA can harm your unborn baby. You and your healthcare provider should decide if you will receive WEZLANA.
- are breastfeeding or plan to breastfeed. WEZLANA can pass into your breast milk.
- Talk to your healthcare provider about the best way to feed your baby if you receive WEZLANA.

Tell your healthcare provider about all the medicines you take, including prescription and over-the-counter medicines, vitamins, and herbal supplements.
Know the medicines you take. Keep a list of them to show your healthcare provider and pharmacist when you get a new medicine.

How should I use WEZLANA?

- Use WEZLANA exactly as the healthcare provider tells you to. The healthcare provider will determine the right dose of WEZLANA, the amount for each injection, and how often it should be given. Be sure to keep all scheduled follow-up appointments.
- The needle cover on the WEZLANA prefilled syringe does not contain latex.
- Adults with Crohn's disease and ulcerative colitis will receive the first dose of WEZLANA through a vein in the arm (intravenous infusion) in a healthcare facility by a healthcare provider. It takes at least 1 hour to receive the full dose of medicine. WEZLANA will then be received as an injection under the skin (subcutaneous injection) 8 weeks after the first dose of WEZLANA, as described below.
- Adults and children 6 years of age and older with plaque psoriasis or psoriatic arthritis will receive WEZLANA as an injection under the skin as described below.
- Injecting WEZLANA under the skin
  - WEZLANA is intended for use under the guidance and supervision of a healthcare provider.
  - In children, it is recommended that WEZLANA be administered by a healthcare provider. If a healthcare provider decides that you or a caregiver may give the injections of WEZLANA at home, you or a caregiver should receive training on the right way to prepare and give the injections.
  - Do not try to inject WEZLANA until you have been shown how to give the injections by a healthcare provider.
  - WEZLANA can be injected under the skin in the upper arms, buttocks, upper legs (thighs) or stomach area (abdomen).
  - Do not give an injection in an area of the skin that is tender, bruised, red or hard.
  - Use a different injection site each time you use WEZLANA.
- If you inject too much WEZLANA, call the healthcare provider or Poison Help line at 1-800-222-1222, or go to the nearest emergency room right away.

Read the detailed Instructions for Use for instructions about how to prepare and inject a dose of WEZLANA, and how to properly throw away (dispose of) used needles, syringes, and vials. The syringe, needle and vial must never be re-used. After the rubber stopper is punctured, WEZLANA can become contaminated by harmful bacteria which could cause an infection if re-used. Therefore, throw away any unused portion of WEZLANA.

What should I avoid while using WEZLANA?
You should avoid receiving a live vaccine during treatment with WEZLANA. See "Before you use or receive WEZLANA, tell your healthcare provider about all of your medical conditions, including if you:"

What are the possible side effects of WEZLANA?
WEZLANA may cause serious side effects, including:

- See "What is the most important information I should know about WEZLANA?"
- Serious allergic reactions. Serious allergic reactions can occur with WEZLANA. Stop using WEZLANA and get medical help right away if you get any of the following symptoms of a serious allergic reaction:

- feeling faint
- swelling of your face, eyelids, tongue, or throat

- chest tightness
- skin rash

- Posterior Reversible Encephalopathy Syndrome (PRES). PRES is a rare condition that affects the brain and can cause death. Tell your healthcare provider right away if you get any symptoms of PRES during treatment with WEZLANA, including:

- headache
- seizures

- confusion
- vision problems

- Lung inflammation. Cases of lung inflammation have happened in some people who receive ustekinumab products, and may be serious. These lung problems may need to be treated in a hospital. Tell your healthcare provider right away if you develop shortness of breath or a cough that doesn't go away during treatment with WEZLANA.

The most common side effects of WEZLANA include:

- nasal congestion, sore throat, and runny nose
- upper respiratory infections
- fever
- headache
- tiredness
- itching
- nausea and vomiting
- influenza

- redness at the injection site
- vaginal yeast infections
- urinary tract infections
- sinus infection
- bronchitis
- diarrhea
- stomach pain
- joint pain

These are not all of the possible side effects of WEZLANA. Call your doctor for medical advice about side effects. You may report side effects to FDA at 1-800-FDA-1088.
You may also report side effects to 1-800-77-AMGEN (1-800-772-6436).

How should I store WEZLANA?

- Store WEZLANA vials and prefilled syringes in a refrigerator between 36°F to 46°F (2°C to 8°C).
- Store WEZLANA in the original carton to protect it from light until time to use it.
- Do not freeze WEZLANA.
- Do not shake WEZLANA.
- If needed, individual WEZLANA prefilled syringe and 45 mg vial may also be stored at room temperature up to 86°F (30°C) for a maximum single period of up to 30 days in the original carton to protect from light.
- Record the date when the prefilled syringe or the 45 mg vial is first removed from the refrigerator on the carton in the space provided.
- After a prefilled syringe or the 45 mg vial has been stored at room temperature, do not return it to the refrigerator.
- Throw away (discard) the prefilled syringe or the 45 mg vial if it is not used within 30 days at room temperature storage.
- Do not use WEZLANA after the expiration date on the carton or on the prefilled syringe or on the 45 mg vial.

Keep WEZLANA and all medicines out of the reach of children.

General information about the safe and effective use of WEZLANA.
Medicines are sometimes prescribed for purposes other than those listed in a Medication Guide. Do not use WEZLANA for a condition for which it was not prescribed. Do not give WEZLANA to other people, even if they have the same symptoms that you have. It may harm them. You can ask your pharmacist or healthcare provider for information about WEZLANA that was written for health professionals.

What are the ingredients in WEZLANA?
Active ingredient: ustekinumab-auub
Inactive ingredients: Single-dose prefilled syringe for subcutaneous use contains histidine, histidine hydrochloride monohydrate, Polysorbate 80, and sucrose. Single-dose vial for subcutaneous use contains histidine, histidine hydrochloride monohydrate, Polysorbate 80 and sucrose. Single-dose vial for intravenous infusion contains edetate disodium, histidine, histidine hydrochloride monohydrate, methionine, Polysorbate 80, and sucrose.
WEZLANA™ (ustekinumab-auub)
Manufactured for Nuvaila, Dublin, Ireland
Manufactured by: Amgen Inc., One Amgen Center Drive, Thousand Oaks, CA 91320-1799 U.S.A.
US License Number 1080
© 2025 Amgen Inc. All rights reserved.
1xxxxxx – v3

This Medication Guide has been approved by the U.S. Food and Drug Administration.

Revised: 10/2025

INSTRUCTIONS FOR USE WEZLANA™ (wez-LAH-nah) (ustekinumab-auub) injection, for subcutaneous use single-dose prefilled syringe

This Instructions for Use contains information on how to inject WEZLANA using a prefilled syringe.

The WEZLANA prefilled syringe is for subcutaneous use only (inject directly under the skin).

Getting to Know Your Prefilled Syringe

Step 1. Important Information You Need to Know Before Injecting WEZLANA

Dosing:

- WEZLANA comes in two different doses: 45 mg and 90 mg. Check your prescription to make sure you have the correct dose.
  - If the dose is 45 mg, you will receive one 45 mg prefilled syringe.
  - If the dose is 90 mg, you will receive either one 90 mg prefilled syringe or two 45 mg prefilled syringes. If you receive two 45 mg prefilled syringes for a 90 mg dose, you will need to give two injections, one right after the other.
- The look of the prefilled syringe will be different for each dose. The amount of medicine in the syringe will also be different for each dose.
- The 45 mg dose will have a smaller amount of medicine and the 90 mg dose will have a larger amount of medicine. Check the figures below to see what your dose looks like in the syringe.

45 mg/0.5 mL

90 mg/mL

Using your WEZLANA prefilled syringe:

- It is important that you do not try to give the injection until you have fully read and understood this Instructions for Use.
- If your healthcare provider decides that you or a caregiver can give your WEZLANA injection at home, you should receive training on the right way to prepare and give the injections. Do not try to inject WEZLANA until you have been shown the right way to give the injections by your healthcare provider.
- Do not use the syringe if the carton is damaged or seal is broken.
- Do not use the syringe after the expiration date on the label.
- Do not shake the syringe.
- Do not remove the needle cap from the syringe until you are ready to inject.
- Do not use the syringe if it has been frozen.
- Do not use the syringe if it has been dropped on a hard surface. Part of the syringe may be broken even if you cannot see the break. Use a new syringe and call 1-800-77-AMGEN (1-800-772-6436).
- The syringe is not made with natural rubber latex.

Important: Keep the syringe and sharps disposal container out of the sight and reach of children.

Frequently asked questions:

For additional information and answers to frequently asked questions, visit www.WEZLANA.com.

Where to get help:

If you want more information or help using WEZLANA:

- Contact your healthcare provider
- Visit www.WEZLANA.com, or
- Call 1-800-77-AMGEN (1-800-772-6436).

Step 2. Storing and Preparing to Inject WEZLANA

2a Refrigerate the syringe carton until you are ready to use it.

- Keep the syringe in the refrigerator between 36°F to 46°F (2°C to 8°C).
- Keep the syringe in the original carton to protect it from light or physical damage until you are ready to use it.
- Do not freeze the syringe.
- Do not store the syringe in extreme heat or cold. For example, avoid storing in your vehicle`s glove box or trunk.

Important: Keep the syringe out of the sight and reach of children.

2b Grasp the syringe by the body and remove it from the carton. To prevent early activation of the needle safety guard, do not touch the NEEDLE GUARD CLIPS at any time during use.

- Do not grab the plunger rod, finger grip or the needle cap.
- Do not grab the needle guard clips.
- Remove the number of syringes you need for your injection.
- Put any unused syringes back into refrigerator.
  WAIT

2c Wait 30 minutes for the syringe to reach room temperature.

- Let the syringe warm up naturally.
- Do not heat with hot water, a microwave, or direct sunlight.
- Do not shake the syringe at any time.
- Using the syringe at room temperature allows for a more comfortable injection.

2d You may also keep WEZLANA at room temperature for up to 30 days, if needed.

- Keep it at room temperature between 68°F to 77°F (20°C to 25°C) for a maximum single period of up to 30 days.
- Do not use WEZLANA if the prefilled syringe has been stored above 86ºF (30ºC).
- Do not put WEZLANA back in refrigerator after it has been stored at room temperature.
- Record the date you removed WEZLANA from the refrigerator and use within 30 days.

Important: Throw away (discard) the syringe in a sharps disposal container if it has reached room temperature and has not been used within 30 days.

2e Gather and place the following items for your injection on a clean, flat, and well-lit surface:

- WEZLANA syringe (room temperature)
- Sharps disposal container (see Step 5. Disposing of WEZLANA and Checking the Injection Site)
- Alcohol wipe
- Adhesive bandage
- Cotton ball or gauze pad

Step 3. Getting Ready for Your Injection

3a Inspect the medicine through the viewing window. It should be clear to white like an opal and colorless to light yellow.

- It is okay to see air bubbles.
- Do not use WEZLANA if the medicine is frozen, cloudy, discolored, or has large particles.

Important: If the medicine is cloudy, discolored or has flakes or if the syringe is damaged or expired, call 1-800-77-AMGEN (1-800-772-6436).

3b Check the expiration (Exp.) date and inspect the syringe for damage.

- Do not use if the expiration date has passed.
- Do not use the syringe if:
  - the needle cap is missing or loose
  - it has cracks or broken parts
  - it has been dropped on a hard surface or dropped without the needle cap in place
- Make sure you have the right medicine and dose.

3c Select the stomach area (abdomen) or upper legs (thighs) for the injection.

- Only a healthcare provider or a caregiver should inject into the back of the upper arm or buttocks.
- Choose a different location (site) for each injection.
- The areas in blue are the recommended injection locations.

Important: Avoid areas where the skin is tender, bruised, red, or hard.

3d Wash your hands thoroughly with soap and water.

3e Clean the injection site with alcohol wipe.

- Let your skin dry on its own.
- Do not touch the clean area again before injecting.

Step 4. Injecting WEZLANA

Important: Only remove the needle cap when you can inject WEZLANA right away (within 5 minutes) because the medicine can dry out.

4a Pull the needle cap straight off while holding the syringe body.

- Do not hold the plunger or plunger head while removing the needle cap.
- Do not twist or bend the needle cap.
- Never put the needle cap back on. It may damage the needle.
- Do not let anything touch the needle after the cap is removed.
- Do not place the syringe on any surface after the cap is removed.
- Do not try to push air bubbles out. It is okay to see air bubbles.
- A drop of medicine at the needle tip is normal.
  PINCH

4b Pinch the skin around injection site before injection.

- Gently pinch the skin with one hand between the thumb and index finger to create a bump for the injection.
- If possible, the bump should be about 2 inches wide.
  Important: Continue to pinch the skin until the injection is complete.
  INSERT

4c Insert the needle into the pinched skin.

- Insert the needle into the pinched skin at about a 45-degree angle.
- Do not place your finger on the plunger rod while inserting the needle, as this may result in lost medicine.
  INJECT

4d Inject all of the liquid by slowly pressing the plunger head all the way down with your thumb until it is completely between the needle guard clips. Hold the finger grips with your fingers as shown in the figure.

- Do not pull back on the plunger rod at any time.
- Do not remove the syringe until all medicine has been injected.
  LIFT

4e Keep pressure on the plunger head with your thumb and remove the needle from your skin.

- Let go of the skin after the needle is removed.
- Slowly take your thumb off the plunger head. This will let the empty syringe move up until the entire needle is automatically covered by the needle guard.

If a second injection is required:

4f Repeat steps 1 to 5 if a second injection is required.

- Check your prescription for your dose.
- If the dose is 90 mg, you will receive either one 90 mg prefilled syringe or two 45 mg prefilled syringes.
  - If you receive two 45 mg prefilled syringes for a 90 mg dose, you will need to give a second injection right after the first injection.
  - Repeat Steps 1 to 5 for the second injection using a new syringe.
  - Choose a different site for the second injection.

Step 5. Disposing of WEZLANA and Checking the Injection Site

Important: Never put the needle cap back on the syringe.

5a Place the used syringe and needle cap in an FDA-cleared sharps disposal container right away after use.

- Do not reuse the syringe.

Important: Do not throw away (dispose of) the syringe in your household trash.

5b Check injection site.

- Do not rub the injection site.
- If there is blood, press a cotton ball or gauze pad on the injection site.
- Apply an adhesive bandage if necessary.

Additional information about your sharps disposal container

If you do not have an FDA-cleared sharps disposal container, you may use a household container that is:

- made of a heavy-duty plastic,
- can be closed with a tight-fitting, puncture-resistant lid, without sharps being able to come out,
- upright and stable during use,
- leak-resistant, and
- properly labeled to warn of hazardous waste inside the container.

Disposing of sharps containers:

When your sharps disposal container is almost full, you will need to follow your community guidelines for the right way to dispose of your sharps disposal container.

There may be state or local laws about how you should throw away used needles and syringes.

For more information about safe sharps disposal, and for specific information about sharps disposal in the state that you live in, go to the FDA's website at: http://www.fda.gov/safesharpsdisposal

Do not dispose of your used sharps disposal container in your household trash unless your community guidelines permit this.
Do not recycle your used sharps disposal container.

For more information or help call 1-800-77-AMGEN (1-800-772-6436).

Manufactured for Nuvaila, Dublin, Ireland

Manufactured by: Amgen Inc., One Amgen Center Drive, Thousand Oaks, California 91320-1799
US License Number 1080

© 2025 Amgen Inc. All rights reserved.

This Instructions for Use has been approved by the U.S. Food and Drug Administration.
Revised: 10/2025

v2

INSTRUCTIONS FOR USE WEZLANA™ (wez-LAH-nah) (ustekinumab-auub) injection, for subcutaneous use single-dose vial

This Instructions for Use contains information on how to inject WEZLANA using a vial.

Read this Instructions for Use before you start using WEZLANA. A healthcare provider should show you how to prepare, measure the dose, and give the injection the right way.

If you cannot give the injection:

- ask a healthcare provider to help you, or
- ask someone who has been trained by a healthcare provider to give the injections.

Do not try to inject WEZLANA until you have been shown the right way to give the injections by a healthcare provider.

Important information You Need to Know Before Injecting WEZLANA:

- For subcutaneous use only (inject directly under the skin).
- Before you start, check the carton to make sure that it is the right dose. You will have either 45 mg or 90 mg as prescribed by the healthcare provider.
  - If the dose is 45 mg or less, you will receive one 45 mg vial.
  - If the dose is 90 mg, you will receive two 45 mg vials and you will need to give two injections, one right after the other.
- Check the expiration date on the vial and carton. If the expiration date has passed, do not use it. If the expiration date has passed, call the healthcare provider or pharmacist, or call 1-800-77-AMGEN (1-800-772-6436) for help.
- Check the vial for any particles or discoloration. The liquid in the vial should look clear to white like an opal and colorless to light yellow.
- Do not use if it is frozen, discolored, cloudy or has large particles. Get a new vial.
- Do not shake the vial at any time. Shaking the vial may damage the WEZLANA medicine. If the vial has been shaken, do not use it. Get a new vial.
- Do not use a WEZLANA vial more than one time, even if there is medicine left in the vial. After the rubber stopper is punctured, WEZLANA can become contaminated by harmful bacteria which could cause an infection if re-used. Therefore, throw away any unused WEZLANA after you give the injection.
- Safely throw away (dispose of) WEZLANA vials, needles, and syringes after use. See "Step 6: Disposing of needles, syringes, and vials."
- Do not re-use syringes or needles.
- To avoid needle-stick injuries, do not recap needles.

Storing WEZLANA vials

- Store WEZLANA vials in a refrigerator between 36°F to 46°F (2°C to 8°C).
- Store WEZLANA vials in the original carton to protect from light until the time of use.
- Do not freeze WEZLANA vials.
- If needed, the WEZLANA vial can also be stored at room temperature up to 86°F (30°C) for a maximum single period of up to 30 days in the original carton to protect from light. Write the date that you removed WEZLANA from the refrigerator on the carton in the space provided.
- Do not use WEZLANA if it has been stored above 86°F (30°C).
- Do not put WEZLANA back in the refrigerator after it has been stored at room temperature.
- Throw away (discard) the vial if it is not used within 30 days of room temperature storage.

Keep WEZLANA and all medicines out of the reach of children.

Gather the supplies you will need to prepare WEZLANA and to give the injection. (See Figure A)

You will need:

- a syringe with the needle attached, you will need a prescription from a healthcare provider to get syringes with the needles attached from a pharmacy
- alcohol wipes
- cotton balls or gauze pads
- adhesive bandage
- your prescribed dose of WEZLANA
- FDA-cleared sharps disposal container. See "Step 6: Dispose of the needles, syringes, and vials."

Figure A

Step 1. Preparing the injection

- Choose a well-lit, clean, flat work surface.
- Wash your hands well with soap and warm water.

Step 2. Preparing your injection site

Figure B

* Areas in blue are recommended injection sites.

- Choose an injection site around the stomach area (abdomen), or upper legs (thighs).
- If a caregiver is giving the injection, the outer area of the upper arms, or the buttocks may also be used. (See Figure B)
- Use a different injection site for each injection. Do not give an injection in an area of the skin that is tender, bruised, red or hard.
- Clean the skin with an alcohol wipe where you plan to give the injection.
- Do not touch this area again before giving the injection. Let the skin dry before injecting.
- Do not fan or blow on the clean area.

Step 3. Preparing the vial

Figure C

3a

- Remove the cap from the top of the vial. Throw away the cap but do not remove the rubber stopper. (See Figure C)

Figure D

3b

- Clean the rubber stopper with an alcohol wipe. (See Figure D)
- Do not touch the rubber stopper after you clean it.
- Put the vial on a flat surface.

Step 4. Preparing the syringe

Figure E

4a

- Pick up the syringe with the needle attached.
- Remove the cap that covers the needle. (See Figure E)
- Throw the needle cap away. Do not touch the needle or allow the needle to touch anything.

Figure F

4b

- Carefully pull back on the plunger to the line that matches the dose prescribed by the healthcare provider.
- Hold the vial between your thumb and index (pointer) finger.
- Use your other hand to push the syringe needle through the center of the rubber stopper. (See Figure F)

Figure G

4c

- Push down on the plunger until all of the air has gone from the syringe into the vial.
- Turn the vial and the syringe upside down. (See Figure G)
- Hold the WEZLANA vial with one hand.
- It is important that the needle is always in the liquid in order to prevent air bubbles forming in the syringe.
- Pull back on the syringe plunger with your other hand.
- Fill the syringe until the black tip of the plunger lines up with the mark that matches the prescribed dose.

Figure H

4d

- Do not remove the needle from the vial. Hold the syringe with the needle pointing up to see if it has any air bubbles inside.
- If there are air bubbles, gently tap the side of the syringe until the air bubbles rise to the top. (See Figure H)
- Slowly press the plunger up until all of the air bubbles are out of the syringe (but none of the liquid is out).
- Remove the syringe from the vial. Do not lay the syringe down or allow the needle to touch anything.

Step 5. Injecting WEZLANA

Figure I

5a

- Hold the barrel of the syringe in one hand, between the thumb and index fingers.
- Do not pull back on the plunger at any time.
- Use the other hand to gently pinch the cleaned area of skin. Hold firmly.
- Use a quick, dart-like motion to insert the needle into the pinched skin at about a 45-degree angle. (See Figure I)

Figure J

5b

- Push the plunger with your thumb as far as it will go to inject all of the liquid. Push it slowly and evenly, keeping the skin gently pinched. (See Figure J)
- When the syringe is empty, pull the needle out of the skin and then let go of the skin.
- When the needle is pulled out of the skin, there may be a little bleeding at the injection site. This is normal. You can press a cotton ball or gauze pad to the injection site if needed. Do not rub the injection site. You may cover the injection site with a small adhesive bandage, if necessary.

If the dose is 90 mg, you will receive two 45 mg vials and you will need to give a second injection right after the first. Repeat Steps 1 to 6 using a new syringe. Choose a different site for the second injection.

Step 6. Disposing of needles, syringes, and vials

- Do not re-use a syringe or needle.
- To avoid needle-stick injuries, do not recap a needle.
- Put the needles and syringes in an FDA-cleared sharps disposal container right away after use. Do not throw away (dispose of) loose needles and syringes in your household trash.
- If you do not have an FDA-cleared sharps disposal container, you may use a household container that is:
  - made of a heavy-duty plastic,
  - can be closed with a tight-fitting, puncture-resistant lid, without sharps being able to come out,
  - upright and stable during use,
  - leak-resistant,
  - and properly labeled to warn of hazardous waste inside the container.
- When your sharps disposal container is almost full, you will need to follow your community guidelines for the right way to dispose of your sharps disposal container. There may be local or state laws about how you should throw away syringes and needles. For more information about safe sharps disposal, and for specific information about sharps disposal in the state that you live in, go to the FDA's website at: http://www.fda.gov/safesharpsdisposal.
- Do not dispose of your used sharps disposal container in your household trash unless your community guidelines permit this. Do not recycle your sharps disposal container.
- Throw away the vial into the container where you put the syringes and needles.
- If you have any questions, talk to your healthcare provider or pharmacist.

Manufactured for Nuvaila, Dublin, Ireland

Manufactured by: Amgen Inc., One Amgen Center Drive, Thousand Oaks, California 91320-1799
US License Number 1080

© 2025 Amgen Inc. All rights reserved.

This Instructions for Use has been approved by the U.S. Food and Drug Administration.
Revised 10/2025

v2

PRINCIPAL DISPLAY PANEL - 45 mg/0.5 mL Syringe Carton - 076-01

NDC 84612-076-01

WEZLANA™
(ustekinumab-auub)
Injection

45
mg/0.5 mL

45 mg/0.5 mL

For Subcutaneous Use Only

ATTENTION: Dispense the enclosed
Medication Guide to each patient.

Sterile Solution - No Preservative

Store refrigerated at 2° to 8°C (36° to 46°F).

Do not shake. Do not freeze.
Keep out of reach of children.
Keep in carton to protect from light.

!
CAUTION: See full prescribing information and
Instructions for Use.

Contains 1 Single-dose Prefilled Syringe
Discard unused portion

Do not re-use
Rx Only

Manufactured for:
nuvaila™

PRINCIPAL DISPLAY PANEL - 90 mg/mL Syringe Carton - 089-01

NDC 84612-089-01

WEZLANA™
(ustekinumab-auub)
Injection

90
mg/mL

90 mg/mL

For Subcutaneous Use Only

ATTENTION: Dispense the enclosed
Medication Guide to each patient.

Sterile Solution - No Preservative

Store refrigerated at 2° to 8°C (36° to 46°F).

Do not shake. Do not freeze.
Keep out of reach of children.
Keep in carton to protect from light.

!
CAUTION: See full prescribing information
and Instructions for Use.

Contains 1 Single-dose Prefilled Syringe
Discard unused portion

Do not re-use
Rx Only

Manufactured for:
nuvaila™

PRINCIPAL DISPLAY PANEL - 45 mg/0.5 mL Vial Carton - 055-01

NDC 84612-055-01

WEZLANA™
(ustekinumab-auub)
Injection

45
mg/0.5 mL

45 mg/0.5 mL

For Subcutaneous Use Only

ATTENTION: Dispense the enclosed
Medication Guide to each patient.

Keep out of reach of children.
Store refrigerated at 2°C to
8°C (36°F to 46°F) in the
original carton to protect
from light. Do not shake. Do
not freeze.
Contains 1 Single-dose Vial
Discard unused portion
Sterile Solution - No
Preservative

Rx Only

Manufactured
for:
nuvaila™

PRINCIPAL DISPLAY PANEL - 130 mg/26 mL Vial Carton

NDC 84612-066-01

WEZLANA™
(ustekinumab-auub)
Injection

130
mg/26 mL

130 mg/26 mL (5 mg/mL)
For Intravenous Infusion Only
Must be diluted
ATTENTION: Dispense the enclosed
Medication Guide to each patient.

Keep out of reach of children.
Store refrigerated at 2°C to
8°C (36°F to 46°F) in the
original carton to protect
from light. Do not shake. Do
not freeze.
Contains 1 Single-dose Vial
Discard unused portion
Sterile Solution - No
Preservative

Rx Only

Manufactured
for:
nuvaila™

PRINCIPAL DISPLAY PANEL - 45 mg/0.5 mL Syringe Carton - 876-01

NDC 84612-876-01

WEZLANA™
(ustekinumab-auub)
Injection

45
mg/0.5 mL

45 mg/0.5 mL

For Subcutaneous Use Only

ATTENTION: Dispense the enclosed
Medication Guide to each patient.

Sterile Solution - No Preservative

Store refrigerated at 2° to 8°C (36° to 46°F).

Do not shake. Do not freeze.
Keep out of reach of children.
Keep in carton to protect from light.

!
CAUTION: See full prescribing information and
Instructions for Use.

Contains 1 Single-dose Prefilled Syringe
Discard unused portion

Do not re-use
Rx Only

Manufactured for:
nuvaila™

PRINCIPAL DISPLAY PANEL - 90 mg/mL Syringe Carton - 889-01

NDC 84612-889-01

WEZLANA™
(ustekinumab-auub)
Injection

90
mg/mL

90 mg/mL

For Subcutaneous Use Only

ATTENTION: Dispense the enclosed
Medication Guide to each patient.

Sterile Solution - No Preservative

Store refrigerated at 2° to 8°C (36° to 46°F).

Do not shake. Do not freeze.
Keep out of reach of children.
Keep in carton to protect from light.

!
CAUTION: See full prescribing information
and Instructions for Use.

Contains 1 Single-dose Prefilled Syringe
Discard unused portion

Do not re-use
Rx Only

Manufactured for:
nuvaila™

PRINCIPAL DISPLAY PANEL - 45 mg/0.5 mL Vial Carton - 855-01

NDC 84612-855-01

WEZLANA™
(ustekinumab-auub)
Injection

45
mg/0.5 mL

45 mg/0.5 mL

For Subcutaneous Use Only

ATTENTION: Dispense the enclosed
Medication Guide to each patient.

Keep out of reach of children.
Store refrigerated at 2°C to
8°C (36°F to 46°F) in the
original carton to protect
from light. Do not shake. Do
not freeze.
Contains 1 Single-dose Vial
Discard unused portion
Sterile Solution - No
Preservative

Rx Only

Manufactured for:
nuvaila™